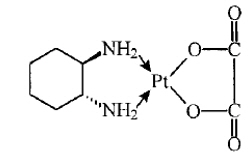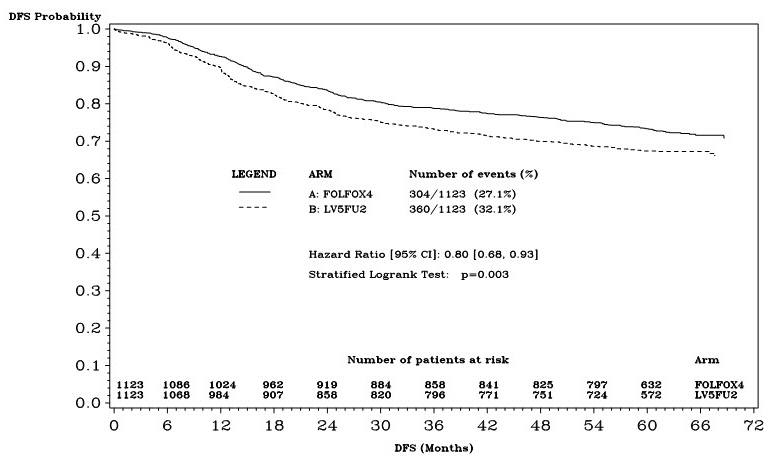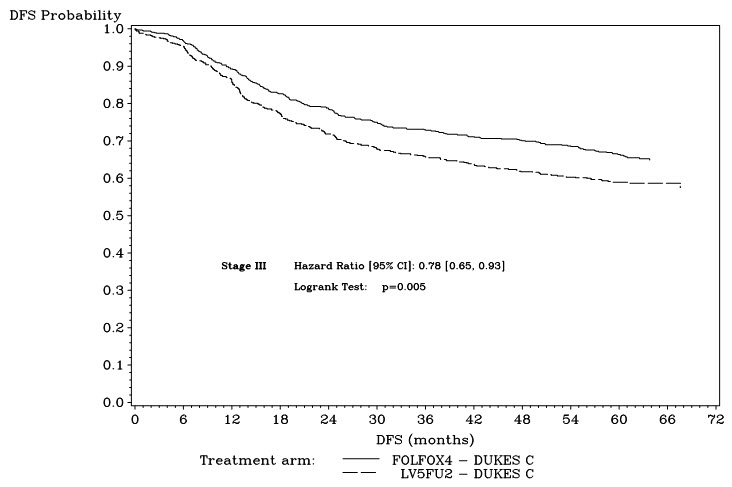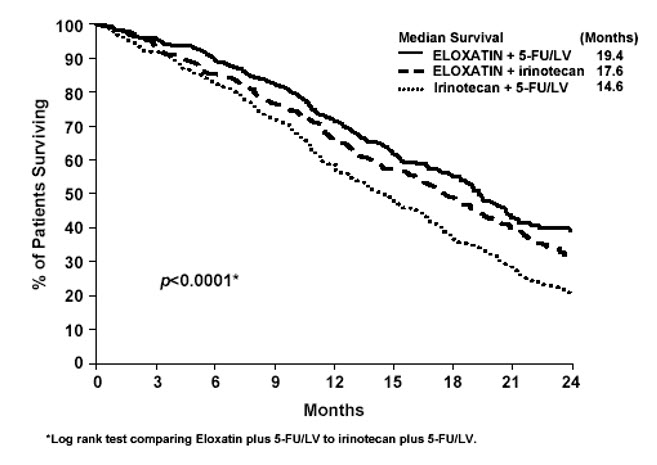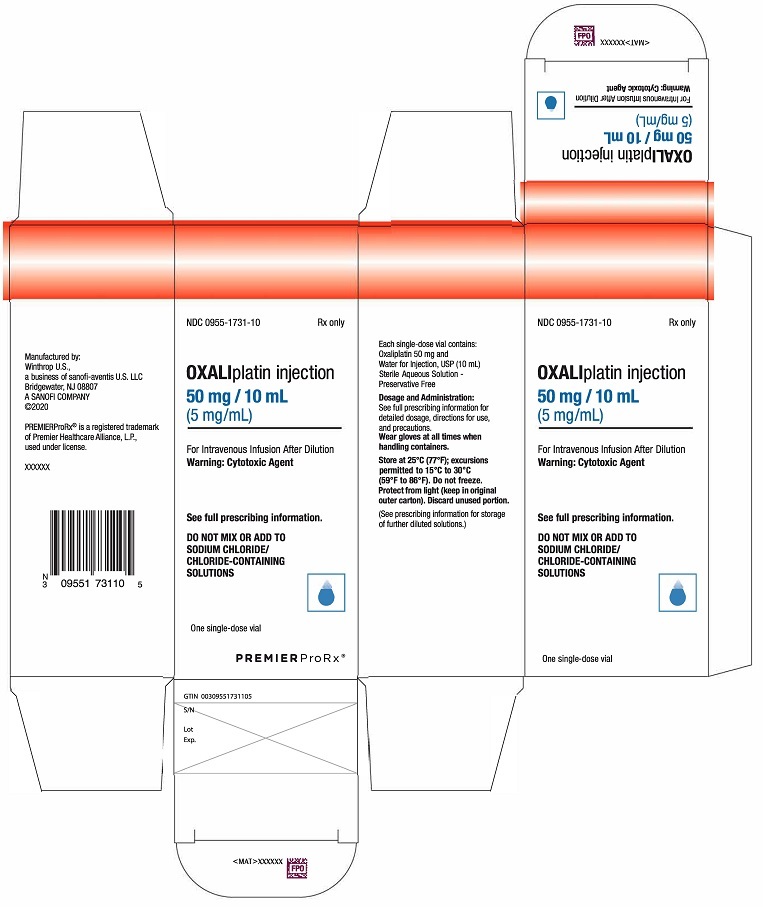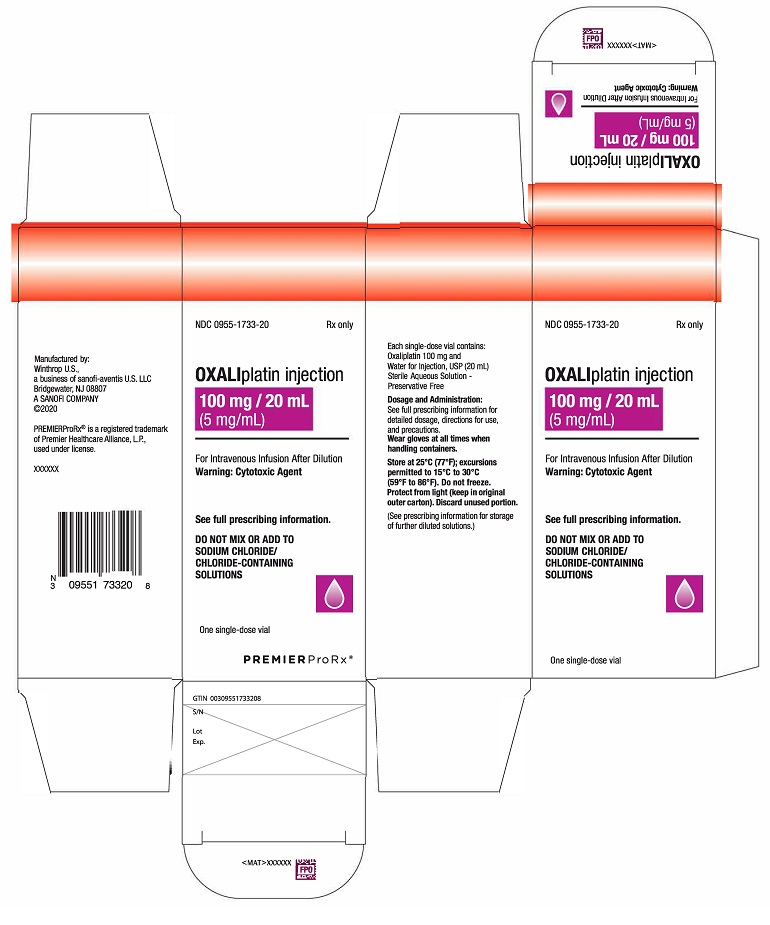 DRUG LABEL: OXALIPLATIN
NDC: 0955-1731 | Form: INJECTION, SOLUTION, CONCENTRATE
Manufacturer: Winthrop U.S, a business of sanofi-aventis U.S. LLC
Category: prescription | Type: HUMAN PRESCRIPTION DRUG LABEL
Date: 20231207

ACTIVE INGREDIENTS: OXALIPLATIN 5 mg/1 mL
INACTIVE INGREDIENTS: WATER

HIGHLIGHTS OF PRESCRIBING INFORMATION

These highlights do not include all the information needed to use oxaliplatin safely and effectively. See full prescribing information for oxaliplatin.
OXALIPLATIN INJECTION, for intravenous use
Initial U.S. Approval: 2002

WARNING: HYPERSENSITIVITY REACTIONS, INCLUDING ANAPHYLAXIS

See full prescribing information for complete boxed warning.

Serious and fatal hypersensitivity adverse reactions, including anaphylaxis, can occur with oxaliplatin within minutes of administration and during any cycle. Oxaliplatin is contraindicated in patients with hypersensitivity reactions to oxaliplatin and other platinum-based drugs. Immediately and permanently discontinue oxaliplatin for hypersensitivity reactions and administer appropriate treatment. (4, 5.1)

1 INDICATIONS AND USAGE

Oxaliplatin is a platinum-based drug used in combination with infusional fluorouracil and leucovorin, which is indicated for:

- adjuvant treatment of stage III colon cancer in patients who have undergone complete resection of the primary tumor. (1)
- treatment of advanced colorectal cancer. (1)

2 DOSAGE AND ADMINISTRATION

- Administer oxaliplatin 85 mg/m^2as an intravenous infusion over 120 minutes concurrently with leucovorin over 120 minutes in separate bags, followed by fluorouracil on Day 1 of each 14-day cycle. Administer fluorouracil and leucovorin on Day 2 as recommended. (2.1)
- Adjuvant Treatment: Continue treatment for up to 12 cycles or unacceptable toxicity. (2.1)
- Advanced Colorectal Cancer: Continue treatment until disease progression or unacceptable toxicity. (2.1)

3 DOSAGE FORMS AND STRENGTHS

Injection: 50 mg (5 mg/mL) or 100 mg (5 mg/mL) in a single-dose vial (3)

4 CONTRAINDICATIONS

- History of hypersensitivity reaction to oxaliplatin or other platinum-based drugs. (4, 5.1)

5 WARNINGS AND PRECAUTIONS

- Peripheral Sensory Neuropathy: Acute and delayed neuropathy can occur. Avoid topical application of ice. Reduce the dose or permanently discontinue oxaliplatin as recommended. (5.2)
- Severe Myelosuppression: Delay oxaliplatin until neutrophils are greater than or equal to 1.5 × 10^9/L and platelets are greater than or equal to 75 × 10^9/L. Withhold oxaliplatin for sepsis or septic shock. Dose reduce after recovery from grade 4 neutropenia, febrile neutropenia, or grade 3–4 thrombocytopenia as recommended. (5.3)
- Posterior Reversible Encephalopathy Syndrome (PRES): Permanently discontinue oxaliplatin in patients who develop PRES. (5.4)
- Pulmonary Toxicity: Withhold oxaliplatin until investigation excludes interstitial lung disease or pulmonary fibrosis. (5.5)
- Hepatotoxicity: Monitor liver function tests at baseline, before each subsequent cycle, and as clinically indicated. (5.6)
- QT Interval Prolongation: Avoid in patients with congenital long QT syndrome. Monitor electrocardiograms in patients with congestive heart failure, bradyarrhythmias, and electrolyte abnormalities, and in patients taking drugs known to prolong the QT interval. Correct electrolyte abnormalities prior to initiating oxaliplatin and periodically during treatment. (5.7)
- Rhabdomyolysis: Permanently discontinue oxaliplatin if rhabdomyolysis occurs. (5.8)
- Hemorrhage: Increase frequency of monitoring in patients who are receiving oxaliplatin with fluorouracil/leucovorin and oral anticoagulants (5.9)
- Embryo-Fetal Toxicity: Can cause fetal harm. Advise pregnant women of the potential risk to a fetus. Advise males and females of reproductive potential to use an effective method of contraception. (5.10, 8.1, 8.3)

6 ADVERSE REACTIONS

Most common adverse reactions (incidence greater than or equal to 40%) were peripheral sensory neuropathy, neutropenia, thrombocytopenia, anemia, nausea, increase in transaminases and alkaline phosphatase, diarrhea, emesis, fatigue, and stomatitis. (6.1)

To report SUSPECTED ADVERSE REACTIONS, contact sanofi-aventis U.S. LLC at 1-800-633-1610 or FDA at 1-800-FDA-1088 or www.fda.gov/medwatch.

8 USE IN SPECIFIC POPULATIONS

- Females: Advise female patients of reproductive potential to use effective contraception while receiving oxaliplatin and for 9 months after the final dose .(8.3)
- Males: Based on its mechanism action as a genotoxic drug, advise males with female partners of reproductive potential to use effective contraception while receiving oxaliplatin and for 6 months after the final dose [see Nonclinical Toxicology (13.1)] .

FULL PRESCRIBING INFORMATION

WARNING: HYPERSENSITIVITY REACTIONS, INCLUDING ANAPHYLAXIS

Serious and fatal hypersensitivity adverse reactions, including anaphylaxis, can occur with oxaliplatin within minutes of administration and during any cycle. Oxaliplatin is contraindicated in patients with hypersensitivity reactions to oxaliplatin and other platinum-based drugs [see Contraindications (4)] . Immediately and permanently discontinue oxaliplatin for hypersensitivity reactions and administer appropriate treatment for management of the hypersensitivity reaction [see Warnings and Precautions (5.1)].

1 INDICATIONS AND USAGE

Oxaliplatin, in combination with infusional fluorouracil and leucovorin, is indicated for:

- adjuvant treatment of stage III colon cancer in patients who have undergone complete resection of the primary tumor.
- treatment of advanced colorectal cancer.

2 DOSAGE AND ADMINISTRATION

2.1 Recommended Dosage

Administer oxaliplatin in combination with fluorouracil and leucovorin every 2 weeks.

- For adjuvant treatment, continue treatment for up to 12 cycles or unacceptable toxicity.
- For advanced colorectal cancer, continue treatment until disease progression or unacceptable toxicity.

Day 1

Administer oxaliplatin 85 mg/m^2as an intravenous infusion over 120 minutes and leucovorin 200 mg/m^2as an intravenous infusion over 120 minutes at the same time in separate bags, followed by fluorouracil 400 mg/m^2as intravenous bolus over 2–4 minutes, followed by fluorouracil 600 mg/m^2as a 22-hour continuous infusion.

Day 2

Administer leucovorin 200 mg/m^2as an intravenous infusion over 120 minutes, followed by fluorouracil 400 mg/m^2as intravenous bolus over 2–4 minutes, followed by fluorouracil 600 mg/m^2as a 22-hour continuous infusion.

Refer to the prescribing information for fluorouracil and leucovorin for additional information.

2.2 Dose Modifications for Adverse Reactions

Prolongation of infusion time for oxaliplatin from 2 hours to 6 hours may mitigate acute toxicities, such as non–life-threatening infusion-related reactions.

Permanently discontinue oxaliplatin for any of the following:

- Hypersensitivity Reactions [see Warnings and Precautions (5.1)]
- Posterior reversible encephalopathy syndrome (PRES) [see Warnings and Precautions (5.4)]
- Confirmed interstitial lung disease or pulmonary fibrosis [see Warnings and Precautions (5.5)]
- Rhabdomyolysis [see Warnings and Precautions (5.8)]

Refer to the fluorouracil and leucovorin prescribing information for dosage modifications for adverse reactions.

Dosage Modifications for Adjuvant Treatment

Dosage modifications for adverse reactions for adjuvant treatment are presented in Table 1.

Table 1: Dosage Modifications for Adjuvant Treatment in Patients with Stage III Colon Cancer
Adverse Reactions | Severity | Oxaliplatin Dosage Modifications
Peripheral Sensory Neuropathy [see Warnings and Precautions (5.2)] | Persistent Grade 2 | Consider reducing oxaliplatin dose to 75 mg/m^2.
Peripheral Sensory Neuropathy [see Warnings and Precautions (5.2)] | Persistent Grade 3 | Consider discontinuing oxaliplatin.
Peripheral Sensory Neuropathy [see Warnings and Precautions (5.2)] | Grade 4 | Discontinue oxaliplatin.
Myelosuppression [see Warnings and Precautions (5.3), Adverse Reactions (6.1)]. | Grade 4 neutropenia or febrile neutropenia | Delay the next dose until neutrophils greater than or equal to 1.5 × 10^9/L and platelets greater than or equal to 75 × 10^9/L. Reduce oxaliplatin dose to 75 mg/m^2.
Myelosuppression [see Warnings and Precautions (5.3), Adverse Reactions (6.1)]. | Grade 3–4 thrombocytopenia | Delay the next dose until neutrophils greater than or equal to 1.5 × 10^9/L and platelets greater than or equal to 75 × 10^9/L. Reduce oxaliplatin dose to 75 mg/m^2.
Gastrointestinal Adverse Reactions [see Adverse Reactions (6.1)] | Grade 3–4 | After recovery, reduce oxaliplatin dose to 75 mg/m^2along with a dose reduction of fluorouracil to 300 mg/m^2as an intravenous bolus and 500 mg/m^2as a 22-hour continuous infusion.

Dosage Modifications for Advanced Colorectal Cancer

Dosage modifications for adverse reactions for advanced colorectal cancer are presented in Table 2.

Table 2: Dosage Modifications for Advanced Colorectal Cancer
Adverse Reactions | Severity | Oxaliplatin Dosage Modifications
Neuropathy [see Warnings and Precautions (5.2)] | Persistent Grade 2 | Consider reducing oxaliplatin dose to 65 mg/m^2.
Neuropathy [see Warnings and Precautions (5.2)] | Persistent Grade 3 | Consider discontinuing oxaliplatin.
Neuropathy [see Warnings and Precautions (5.2)] | Grade 4 | Discontinue oxaliplatin.
Myelosuppression [see Warnings and Precautions (5.3), Adverse Reactions (6.1)] | Grade 4 neutropenia or febrile neutropenia | Delay the next dose until neutrophils greater than or equal to 1.5 × 10^9/L and platelets greater than or equal to 75 × 10^9/L. Reduce oxaliplatin dose to 65 mg/m^2.
Myelosuppression [see Warnings and Precautions (5.3), Adverse Reactions (6.1)] | Grade 3–4 thrombocytopenia | Delay the next dose until neutrophils greater than or equal to 1.5 × 10^9/L and platelets greater than or equal to 75 × 10^9/L. Reduce oxaliplatin dose to 65 mg/m^2.
Gastrointestinal Adverse Reactions [see Adverse Reactions (6.1)] | Grade 3–4 | After recovery, reduce oxaliplatin dose to 65 mg/ m^2along with a dose reduction of fluorouracil to 300 mg/m^2as an intravenous bolus and 500 mg/m^2as a 22-hour continuous infusion .

2.3 Dose Modifications for Patients with Renal Impairment

In patients with severe renal impairment (creatinine clearance [CLcr] less than 30 mL/min, calculated by the Cockcroft-Gault equation), reduce the oxaliplatin dose to 65 mg/m^2 [see Use in Specific Populations (8.6), Clinical Pharmacology (12.3)] .

2.4 Preparation and Administration

- Oxaliplatin is a cytotoxic drug. Follow applicable special handling and disposal procedures.^1
- Do not freeze.
- Protect the concentrated solution from light.
- Dilute concentrated solution with 250 to 500 mL of 5% Dextrose Injection, USP. Do not dilute with sodium chloride solution or other chloride-containing solutions.
- Store diluted solution for no more than 6 hours at room temperature (20°C to 25°C [68°F to 77°F]) or 24 hours under refrigeration (2°C to 8°C [36°F to 46°F]). Protection from light is not required.
- Visually inspect for particulate matter and discoloration prior to administration and discard if present.
- Do not mix oxaliplatin or administer oxaliplatin through the same infusion line concurrently with alkaline medications or media (such as basic solutions of fluorouracil).
- Flush the infusion line with 5% Dextrose Injection, USP prior to administration of any concomitant medication.
- Do not use needles or intravenous administration sets containing aluminum parts for the preparation or mixing of oxaliplatin. Aluminum has been reported to cause degradation of platinum compounds.
- Administer oxaliplatin as an intravenous infusion over 120 minutes concurrently with leucovorin over 120 minutes in separate bags.

3 DOSAGE FORMS AND STRENGTHS

Injection: 50 mg (5 mg/mL) or 100 mg (5 mg/mL) clear, colorless solution in a single-dose vial.

4 CONTRAINDICATIONS

Oxaliplatin is contraindicated in patients with a history of a hypersensitivity reaction to oxaliplatin or other platinum-based drugs. Reactions have included anaphylaxis [see Warnings and Precautions (5.1)] .

5 WARNINGS AND PRECAUTIONS

5.1 Hypersensitivity Reactions

Serious and fatal hypersensitivity reactions, including anaphylaxis, can occur with oxaliplatin within minutes of administration and during any cycle. Grade 3–4 hypersensitivity reactions, including anaphylaxis, occurred in 2% to 3% of patients with colon cancer who received oxaliplatin. Hypersensitivity reactions, including rash, urticaria, erythema, pruritus, and rarely, bronchospasm and hypotension, were similar in nature and severity to those reported with other platinum-based drugs.

Oxaliplatin is contraindicated in patients with hypersensitivity reactions to platinum-based drugs [see Contraindications (4)] . Immediately and permanently discontinue oxaliplatin for hypersensitivity reactions and administer appropriate treatment for management of hypersensitivity reactions.

5.2 Peripheral Sensory Neuropathy

Oxaliplatin can cause acute and delayed neuropathy. Reduce the dose or permanently discontinue oxaliplatin for persistent neurosensory reactions based on the severity of the adverse reaction [see Dosage and Administration (2.2)] .

Acute Neuropathy

Acute neuropathy typically presents as a reversible, primarily peripheral sensory neuropathy that occurs within hours or 2 days following a dose, resolves within 14 days, and frequently recurs with further dosing. The symptoms can be precipitated or exacerbated by exposure to cold temperature or cold objects and they usually present as transient paresthesia, dysesthesia and hypoesthesia in the hands, feet, perioral area, or throat. Jaw spasm, abnormal tongue sensation, dysarthria, eye pain, and a feeling of chest pressure have also been observed. The acute, reversible pattern of sensory neuropathy was observed in about 56% of patients who received oxaliplatin with fluorouracil/leucovorin. In any individual cycle, acute neuropathy occurred in approximately 30% of patients. For grade 3 peripheral sensory neuropathy, the median time to onset was 9 cycles for adjuvant treatment and 6 cycles for previously treated advanced colorectal cancer.

An acute syndrome of pharyngolaryngeal dysesthesia occurred in 1% to 2% (grade 3–4) of patients previously untreated for advanced colorectal cancer. Subjective sensations of dysphagia or dyspnea, without any laryngospasm or bronchospasm (no stridor or wheezing) occurred in patients previously treated for advanced colorectal cancer.

Avoid topical application of ice for mucositis prophylaxis or other conditions, because cold temperature can exacerbate acute neurological symptoms .

Delayed Neuropathy

Delayed neuropathy typically presents as a persistent (greater than 14 days), primarily peripheral sensory neuropathy that is usually characterized by paresthesias, dysesthesias, and hypoesthesias, but may also include deficits in proprioception that can interfere with daily activities (e.g., writing, buttoning, swallowing, and difficulty walking from impaired proprioception). These forms of neuropathy occurred in 48% of patients receiving oxaliplatin. Delayed neuropathy can occur without any prior acute neuropathy. Most patients (80%) who developed grade 3 persistent neuropathy progressed from prior grade 1 or 2 reactions. These symptoms may improve in some patients upon discontinuation of oxaliplatin.

Adjuvant treatment

In the adjuvant treatment trial, neuropathy was graded using NCI CTC, version 1 as summarized in Table 3.

Table 3: Grading for Neuropathy in Adjuvant Treatment Trial
Grade | Definition
0 | No change or none
1 | Mild paresthesias, loss of deep tendon reflexes
2 | Mild or moderate objective sensory loss, moderate paresthesias
3 | Severe objective sensory loss or paresthesias that interfere with function
4 | Not applicable

Peripheral sensory neuropathy occurred in 92% of patients (all grades), including 13% of patients (grade 3) who received oxaliplatin with fluorouracil/leucovorin. At the 28-day follow-up after the last treatment cycle, 60% of patients had any grade (grade 1=40%, grade 2=16%, grade 3=5%) peripheral sensory neuropathy, decreasing to 39% at 6 months of follow-up (grade 1=31%, grade 2=7%, grade 3=1%) and 21% at 18 months of follow-up (grade 1=17%, grade 2=3%, grade 3=1%).

Advanced colorectal cancer

In the advanced colorectal cancer trials, neuropathy was graded using the neurotoxicity scale summarized in Table 4.

Table 4: Grading for Neuropathy in Advanced Colorectal Cancer Trials
Grade | Definition
1 | Resolved and did not interfere with functioning
2 | Interfered with function but not daily activities
3 | Pain or functional impairment that interfered with daily activities
4 | Persistent impairment that is disabling or life-threatening

Neuropathy occurred in 82% (all grades) of patients previously untreated for advanced colorectal cancer, including 19% grade 3–4; and in 74% (all grades) of patients previously treated for advanced colorectal cancer, including 7% grade 3–4.

5.3 Severe Myelosuppression

Grade 3 or 4 neutropenia occurred in 41% to 44% of patients with colorectal cancer who received oxaliplatin with fluorouracil/leucovorin. Sepsis, neutropenic sepsis and septic shock, including fatal outcomes, occurred in patients who received oxaliplatin [see Adverse Reactions (6.1, 6.2)] .

Grade 3 or 4 thrombocytopenia occurred in 2% to 5% of patients with colorectal cancer who received oxaliplatin with fluorouracil/leucovorin.

Monitor complete blood cell count at baseline, before each subsequent cycle and as clinically indicated .Delay oxaliplatin until neutrophils are greater than or equal to 1.5 × 10^9/L and platelets are greater than or equal to 75 × 10^9/L. Withhold oxaliplatin for sepsis or septic shock. Dose reduce oxaliplatin after recovery from grade 4 neutropenia, febrile neutropenia or grade 3–4 thrombocytopenia as recommended [see Dosage and Administration (2.2)] .

5.4 Posterior Reversible Encephalopathy Syndrome

PRES occurred in less than 0.1% of patients across clinical trials [see Adverse Reactions (6.1)] . Signs and symptoms of PRES can include headache, altered mental functioning, seizures, abnormal vision from blurriness to blindness, associated or not with hypertension. Confirm the diagnosis of PRES with magnetic resonance imaging. Permanently discontinue oxaliplatin in patients who develop PRES.

5.5 Pulmonary Toxicity

Oxaliplatin has been associated with pulmonary fibrosis (less than 1% of patients), which may be fatal [see Adverse Reactions (6.1)] .

In the adjuvant treatment trial, the combined incidence of cough and dyspnea was 7.4% (any grade), including less than 1% (grade 3) in the oxaliplatin arm. One patient died from eosinophilic pneumonia in the oxaliplatin arm.

In the previously untreated advanced colorectal cancer trial, the combined incidence of cough, dyspnea, and hypoxia was 43% (any grade), including 7% (grade 3–4) in the oxaliplatin with fluorouracil/leucovorin arm.

In case of unexplained respiratory symptoms, such as non-productive cough, dyspnea, crackles, or radiological pulmonary infiltrates, withhold oxaliplatin until further pulmonary investigation excludes interstitial lung disease or pulmonary fibrosis. Permanently discontinue oxaliplatin for confirmed interstitial lung disease or pulmonary fibrosis.

5.6 Hepatotoxicity

In the adjuvant treatment trial, increased transaminases (57% vs 34%) and alkaline phosphatase (42% vs 20%) occurred more commonly in the oxaliplatin arm than in the fluorouracil/leucovorin arm [see Adverse Reactions (6.1)] . The incidence of increased bilirubin was similar on both arms. Changes noted on liver biopsies include: peliosis, nodular regenerative hyperplasia or sinusoidal alterations, perisinusoidal fibrosis, and veno-occlusive lesions.

Consider evaluating patients who develop abnormal liver tests or portal hypertension, which cannot be explained by liver metastases, for hepatic vascular disorders. Monitor liver function tests at baseline, before each subsequent cycle, and as clinically indicated.

5.7 QT Interval Prolongation and Ventricular Arrhythmias

QT prolongation and ventricular arrhythmias, including fatal torsade de pointes, have been reported with oxaliplatin [see Adverse Reactions (6.2)] .

Avoid oxaliplatin in patients with congenital long QT syndrome. Monitor electrocardiograms (ECG) in patients with congestive heart failure, bradyarrhythmias, and electrolyte abnormalities and in patients taking drugs known to prolong the QT interval, including Class Ia and III antiarrhythmics [see Drug Interactions (7.1)] . Monitor and correct electrolyte abnormalities prior to initiating oxaliplatin and periodically during treatment.

5.8 Rhabdomyolysis

Rhabdomyolysis, including fatal cases, has been reported with oxaliplatin [see Adverse Reactions (6.2)] . Permanently discontinue oxaliplatin for any signs or symptoms of rhabdomyolysis.

5.9 Hemorrhage

The incidence of hemorrhage in clinical trials was higher on the oxaliplatin combination arm compared to the fluorouracil/leucovorin arm. These reactions included gastrointestinal bleeding, hematuria, and epistaxis. In the adjuvant treatment trial, 2 patients died from intracerebral hemorrhage [see Adverse Reactions (6.1)] .

Prolonged prothrombin time and INR occasionally associated with hemorrhage have been reported in patients who received oxaliplatin with fluorouracil/leucovorin while on anticoagulants [see Adverse Reactions (6.2)] . Increase frequency of monitoring in patients who are receiving oxaliplatin with fluorouracil/leucovorin and oral anticoagulants [see Drug Interactions (7.3)] .

Thrombocytopenia and immune-mediated thrombocytopenia have been observed with oxaliplatin. Rapid onset of thrombocytopenia and greater risk of bleeding have been observed in immune-mediated thrombocytopenia. In this case, consider discontinuing oxaliplatin.

5.10 Embryo-Fetal Toxicity

Based on findings from animal studies and its mechanism of action, oxaliplatin can cause fetal harm when administered to a pregnant woman. The available human data do not establish the presence or absence of major birth defects or miscarriage related to the use of oxaliplatin. Reproductive toxicity studies demonstrated adverse effects on embryo-fetal development in rats at maternal doses that were below the recommended human dose based on body surface area. Advise pregnant women of the potential risk to a fetus. Advise females of reproductive potential to use effective contraception during treatment with oxaliplatin and for 9 months after the final dose. Advise males with female partners of reproductive potential to use effective contraception during treatment with oxaliplatin and for 6 months after the final dose [see Use in Specific Populations (8.1, 8.3)].

6 ADVERSE REACTIONS

The following clinically significant adverse reactions are described elsewhere in labeling:

- Hypersensitivity Reactions [see Warnings and Precautions (5.1)]
- Peripheral Sensory Neuropathy [see Warnings and Precautions (5.2)]
- Severe Myelosuppression [see Warnings and Precautions (5.3)]
- Reversible Posterior Leukoencephalopathy Syndrome [see Warnings and Precautions (5.4)]
- Pulmonary Toxicity [see Warnings and Precautions (5.5)]
- Hepatotoxicity [see Warnings and Precautions (5.6)]
- QT Interval Prolongation and Ventricular Arrhythmias [see Warnings and Precautions (5.7)]
- Rhabdomyolysis [see Warnings and Precautions (5.8)]
- Hemorrhage [see Warnings and Precautions (5.9)]

6.1 Clinical Trials Experience

Because clinical trials are conducted under widely varying conditions, adverse reaction rates observed in the clinical trials of a drug cannot be directly compared to rates in the clinical trials of another drug and may not reflect the rates observed in practice.

More than 1100 patients with stage II or III colon cancer and more than 4,000 patients with advanced colorectal cancer were treated in trials with oxaliplatin. The most common adverse reactions in patients with stage II or III colon cancer receiving adjuvant treatment were peripheral sensory neuropathy, neutropenia, thrombocytopenia, anemia, nausea, increase in transaminases and alkaline phosphatase, diarrhea, emesis, fatigue and stomatitis. The most common adverse reactions in previously untreated and treated patients with advanced colorectal cancer were peripheral sensory neuropathies, fatigue, neutropenia, nausea, emesis, and diarrhea.

Adjuvant Treatment

The safety of oxaliplatin in combination with fluorouracil (FU)/leucovorin (LV) was evaluated in patients with stage II or III colon cancer, who had undergone complete resection of the primary tumor in the adjuvant treatment trial [see Clinical Studies (14.1)].

Fatal adverse reactions in patients who received oxaliplatin in the combination arm included sepsis/neutropenic sepsis (n=3), intracerebral hemorrhage (n=2), and eosinophilic pneumonia (n=1).

Thromboembolic events occurred in 6% (grade 3–4, 1.2%) of patients in the oxaliplatin arm.

Grade 3 or 4 adverse reactions occurred in 70% of patients in the oxaliplatin arm. Grade 3–4 gastrointestinal bleeding occurred in 0.2% of patients. Febrile neutropenia occurred in 0.7% and documented infection with concomitant grade 3–4 neutropenia occurred in 1.1%.

Discontinuation due to an adverse reaction occurred in 15% of the patients in the oxaliplatin arm.

Tables 5, 6, and 7 summarize the adverse reactions reported in patients with colon cancer receiving adjuvant treatment.

Table 5: Adverse Reactions Reported in Patients with Colon Cancer Receiving Adjuvant Treatment (greater than or equal to 5% of all patients and with greater than or equal to 1% grade 3–4)
 | Oxaliplatin + FU/LV N=1108 |  | FU/LV N=1111
Adverse Reaction [Event coded in WHO-ART dictionary] | All Grades (%) | Grade 3–4 (%) | All Grades (%) | Grade 3–4 (%)
Neurology
Peripheral Sensory Neuropathy | 92 | 12 | 16 | <1
Gastrointestinal
Nausea | 74 | 5 | 61 | 2
Diarrhea | 56 | 11 | 48 | 7
Vomiting | 47 | 6 | 24 | 1
Stomatitis | 42 | 3 | 40 | 2
Anorexia | 13 | 1 | 8 | <1
Constitutional Symptoms/Pain
Fatigue | 44 | 4 | 38 | 1
Abdominal Pain | 18 | 1 | 17 | 2
Dermatology/Skin
Skin Disorder | 32 | 2 | 36 | 2
Injection Site Reaction [Includes thrombosis related to the catheter] | 11 | 3 | 10 | 3
Fever/Infection
Fever | 27 | 1 | 12 | 1
Infection | 25 | 4 | 25 | 3
Allergy/Immunology
Allergic Reaction | 10 | 3 | 2 | <1

Table 6: Adverse Reactions Reported in Patients with Colon Cancer Receiving Adjuvant Treatment (greater than or equal to 5% of all patients but with less than 1% grade 3–4)
 | Oxaliplatin + FU/LV N=1108 | FU/LV N=1111
Adverse Reaction [Event coded in WHO-ART dictionary] | All Grades (%) | All Grades (%)
Dermatology/Skin
Alopecia [No complete alopecia was reported] | 30 | 28
Gastrointestinal
Constipation | 22 | 19
Taste Perversion | 12 | 8
Dyspepsia | 8 | 5
Constitutional Symptoms/Pain/Ocular/Visual
Epistaxis | 16 | 12
Weight Increase | 10 | 10
Conjunctivitis | 9 | 15
Headache | 7 | 5
Dyspnea | 5 | 3
Pain | 5 | 5
Abnormal Lacrimation | 4 | 12
Neurology
Sensory Disturbance | 8 | 1
Allergy/Immunology
Rhinitis | 6 | 8

In females, the following grade 3–4 adverse reactions were more frequent: diarrhea, fatigue, neutropenia, nausea, and vomiting.

In patients greater than or equal to 65 years old, the incidence of grade 3–4 diarrhea and neutropenia was higher than in younger adults.

Clinically relevant adverse reactions were reported in greater than or equal to 2% and less than 5% of the patients in the oxaliplatin arm (listed in decreasing order of frequency) were pain, leukopenia, weight loss, and cough.

Table 7: Laboratory-Related Adverse Reactions Occurring in ≥5% of Patients with Colon Cancer Receiving Adjuvant Treatment
Laboratory-Related Adverse Reaction | Oxaliplatin with FU/LV N=1108 |  | FU/LV N=1111
Laboratory-Related Adverse Reaction | All Grades (%) | Grades 3–4 (%) | All Grades (%) | Grades 3–4 (%)
Hematology
Neutropenia | 79 | 41 | 40 | 5
Thrombocytopenia | 77 | 2 | 19 | <1
Anemia | 76 | 1 | 67 | <1
Hepatic
Increased Transaminases | 57 | 2 | 34 | 1
Increased Alkaline Phosphatase | 42 | <1 | 20 | <1
Hyperbilirubinemia | 20 | 4 | 20 | 5

Previously Untreated Advanced Colorectal Cancer

The safety of oxaliplatin in combination with fluorouracil (FU)/leucovorin (LV) was evaluated in a randomized trial of patients with previously untreated advanced colorectal cancer [see Clinical Studies (14.2)] . The adverse reaction profile in this trial was similar to that seen in other trials.

Tables 8, 9, and 10 summarize the adverse reactions reported in the previously untreated advanced colorectal cancer trial.

Table 8: Adverse Reactions Reported in Patients in the Previously Untreated Advanced Colorectal Cancer Clinical Trial (greater than or equal to 5% of all patients and with greater than or equal to 1% grade 3–4)
Adverse Reaction [Event coded in WHO-ART dictionary] | Oxaliplatin + FU/LV N=259 |  | Irinotecan + FU/LV N=256 |  | Oxaliplatin + Irinotecan N=258
Adverse Reaction [Event coded in WHO-ART dictionary] | All Grades (%) | Grades 3–4 (%) | All Grades (%) | Grades 3–4 (%) | All Grades (%) | Grades 3–4 (%)
Neurology
Neuropathy | 82 | 19 | 18 | 2 | 69 | 7
Paresthesias | 77 | 18 | 16 | 2 | 62 | 6
Pharyngo-laryngeal Dysesthesias | 38 | 2 | 1 | 0 | 28 | 1
Neuro-sensory | 12 | 1 | 2 | 0 | 9 | 1
Neuro NOS [Not otherwise specified] | 1 | 0 | 1 | 0 | 1 | 0
Gastrointestinal
Nausea | 71 | 6 | 67 | 15 | 83 | 19
Diarrhea | 56 | 12 | 65 | 29 | 76 | 25
Vomiting | 41 | 4 | 43 | 13 | 64 | 23
Stomatitis | 38 | 0 | 25 | 1 | 19 | 1
Anorexia | 35 | 2 | 25 | 4 | 27 | 5
Constipation | 32 | 4 | 27 | 2 | 21 | 2
Diarrhea-colostomy | 13 | 2 | 16 | 7 | 16 | 3
Gastrointestinal NOS | 5 | 2 | 4 | 2 | 3 | 2
Constitutional Symptoms/Pain/Ocular/Visual
Fatigue | 70 | 7 | 58 | 11 | 66 | 16
Abdominal Pain | 29 | 8 | 31 | 7 | 39 | 10
Myalgia | 14 | 2 | 6 | 0 | 9 | 2
Pain | 7 | 1 | 5 | 1 | 6 | 1
Abnormal Vision | 5 | 0 | 2 | 1 | 6 | 1
Neuralgia | 5 | 0 | 0 | 0 | 2 | 1
Pulmonary
Cough | 35 | 1 | 25 | 2 | 17 | 1
Dyspnea | 18 | 7 | 14 | 3 | 11 | 2
Hiccups | 5 | 1 | 2 | 0 | 3 | 2
Hepatic/Metabolic/Laboratory/Renal
Hyperglycemia | 14 | 2 | 11 | 3 | 12 | 3
Hypokalemia | 11 | 3 | 7 | 4 | 6 | 2
Dehydration | 9 | 5 | 16 | 11 | 14 | 7
Hypoalbuminemia | 8 | 0 | 5 | 2 | 9 | 1
Hyponatremia | 8 | 2 | 7 | 4 | 4 | 1
Urinary Frequency | 5 | 1 | 2 | 1 | 3 | 1
Hematology/Infection
Infection Normal ANC [Absolute neutrophil count] | 10 | 4 | 5 | 1 | 7 | 2
Infection Low ANC | 8 | 8 | 12 | 11 | 9 | 8
Lymphopenia | 6 | 2 | 4 | 1 | 5 | 2
Febrile Neutropenia | 4 | 4 | 15 | 14 | 12 | 11
Dermatology/Skin
Hand/Foot Syndrome | 7 | 1 | 2 | 1 | 1 | 0
Injection Site Reaction | 6 | 0 | 1 | 0 | 4 | 1
Cardiovascular
Thrombosis | 6 | 5 | 6 | 6 | 3 | 3
Hypotension | 5 | 3 | 6 | 3 | 4 | 3

Table 9: Adverse Reactions Reported in Patients in the Previously Untreated Advanced Colorectal Cancer Clinical Trial (greater than or equal to 5% of all patients but with less than 1% grade 3–4)
Adverse Reaction [Event coded in WHO-ART dictionary] | Oxaliplatin + FU/LV N=259 | Irinotecan + FU/LV N=256 | Oxaliplatin + Irinotecan N=258
Adverse Reaction [Event coded in WHO-ART dictionary] | All Grades (%) | All Grades (%) | All Grades (%)
Dermatology/Skin
Alopecia [No complete alopecia was reported] | 38 | 44 | 67
Flushing | 7 | 2 | 5
Pruritus | 6 | 4 | 2
Dry Skin | 6 | 2 | 5
Hematology/Infection
Fever Normal ANC [Absolute neutrophil count] | 16 | 9 | 9
Cardiovascular
Edema | 15 | 13 | 10
Gastrointestinal
Taste Perversion | 14 | 6 | 8
Dyspepsia | 12 | 7 | 5
Flatulence | 9 | 6 | 5
Mouth Dryness | 5 | 2 | 3
Constitutional Symptoms/Pain/Ocular/Visual
Headache | 13 | 6 | 9
Weight Loss | 11 | 9 | 11
Epistaxis | 10 | 2 | 2
Tearing | 9 | 1 | 2
Rigors | 8 | 2 | 7
Dysphasia | 5 | 3 | 3
Sweating | 5 | 6 | 12
Arthralgia | 5 | 5 | 8
Neurology
Insomnia | 13 | 9 | 11
Depression | 9 | 5 | 7
Dizziness | 8 | 6 | 10
Anxiety | 5 | 2 | 6
Allergy/Immunology
Rash | 11 | 4 | 7
Rhinitis Allergic | 10 | 6 | 6
Hepatic/Metabolic/Laboratory/Renal
Hypocalcemia | 7 | 5 | 4
Elevated Creatinine | 4 | 4 | 5

Clinically relevant adverse reactions that occurred in greater than or equal to 2% and less than 5% of the patients in the oxaliplatin and fluorouracil/leucovorin combination arm (listed in decreasing order of frequency) were: metabolic, pneumonitis, catheter infection, vertigo, prothrombin time, pulmonary, rectal bleeding, dysuria, nail changes, chest pain, rectal pain, syncope, hypertension, hypoxia, unknown infection, bone pain, pigmentation changes, and urticaria.

Table 10: Laboratory-Related Adverse Reactions Occurring in ≥5% of Patients in the Previously Untreated Advanced Colorectal Cancer Trial
Laboratory-Related Adverse Reaction | Oxaliplatin and FU/LV N=259 |  | Irinotecan and FU/LV N=256 |  | Oxaliplatin and Irinotecan N=258
Laboratory-Related Adverse Reaction | All Grades (%) | Grades 3–4 (%) | All Grades (%) | Grades 3–4 (%) | All Grades (%) | Grades 3–4 (%)
Hematology
Leukopenia | 85 | 20 | 84 | 23 | 76 | 24
Neutropenia | 81 | 53 | 77 | 44 | 71 | 36
Thrombocytopenia | 71 | 5 | 26 | 2 | 44 | 4
Anemia | 27 | 3 | 28 | 4 | 25 | 3
Hepatic
Increased AST [Aspartate transaminase] | 17 | 1 | 2 | 1 | 11 | 1
Increased Alkaline Phosphatase | 16 | 0 | 8 | 0 | 14 | 2
Hyperbilirubinemia | 6 | 1 | 3 | 1 | 3 | 2
Increased ALT [Alanine transaminase] | 6 | 1 | 2 | 0 | 5 | 2

Previously Treated Advanced Colorectal Cancer

The safety of oxaliplatin in combination with fluorouracil (FU)/leucovorin (LV) was evaluated in a randomized trial in patients with refractory and relapsed colorectal cancer [see Clinical Studies (14.3)] . The adverse reaction profile in this trial was similar to that seen in other trials.

Three patients who received oxaliplatin in the combination arm experienced fatal adverse reactions: gastrointestinal bleeding and dehydration.

Grade 3 and 4 neutropenia were reported in 27% and 17% of patients, respectively, in the oxaliplatin with fluorouracil/leucovorin combination arm. Grade 3–4 increased serum creatinine occurred in 1% of patients in the oxaliplatin with combination fluorouracil/leucovorin arm.

Thirteen percent of patients in the oxaliplatin with fluorouracil/leucovorin combination arm discontinued treatment; the most frequent reasons were gastrointestinal adverse reactions, hematologic adverse reactions and neuropathies.

Tables 11, 12, and 13 summarize the adverse reactions reported in the previously treated advanced colorectal cancer trial.

Table 11: Adverse Reactions Reported in Patients in the Previously Treated Advanced Colorectal Cancer Trial (greater than or equal to 5% of all patients and with greater than or equal to 1% grade 3–4)
Adverse Reaction [Event coded in WHO-ART dictionary] | Oxaliplatin + FU/LV N=150 |  | Oxaliplatin N=153 |  | FU/LV N=142
Adverse Reaction [Event coded in WHO-ART dictionary] | All Grades (%) | Grades 3–4 (%) | All Grades (%) | Grades 3–4 (%) | All Grades (%) | Grades 3–4 (%)
Neurology
Neuropathy | 74 | 7 | 76 | 7 | 17 | 0
Acute | 56 | 2 | 65 | 5 | 10 | 0
Persistent | 48 | 6 | 43 | 3 | 9 | 0
Constitutional Symptoms/Pain
Fatigue | 68 | 7 | 61 | 9 | 52 | 6
Back Pain | 19 | 3 | 11 | 0 | 16 | 4
Pain | 15 | 2 | 14 | 3 | 9 | 3
Gastrointestinal
Diarrhea | 67 | 11 | 46 | 4 | 44 | 3
Nausea | 65 | 11 | 64 | 4 | 59 | 4
Vomiting | 40 | 9 | 37 | 4 | 27 | 4
Stomatitis | 37 | 3 | 14 | 0 | 32 | 3
Abdominal Pain | 33 | 4 | 31 | 7 | 31 | 5
Anorexia | 29 | 3 | 20 | 2 | 20 | 1
Gastroesophageal Reflux | 5 | 2 | 1 | 0 | 3 | 0
Hematology/Infection
Fever | 29 | 1 | 25 | 1 | 23 | 1
Febrile Neutropenia | 6 | 6 | 0 | 0 | 1 | 1
Cardiovascular
Dyspnea | 20 | 4 | 13 | 7 | 11 | 2
Coughing | 19 | 1 | 11 | 0 | 9 | 0
Edema | 15 | 1 | 10 | 1 | 13 | 1
Thromboembolism | 9 | 8 | 2 | 1 | 4 | 2
Chest Pain | 8 | 1 | 5 | 1 | 4 | 1
Dermatology/Skin
Injection Site Reaction | 10 | 3 | 9 | 0 | 5 | 1
Hepatic/Metabolic/Laboratory/Renal
Hypokalemia | 9 | 4 | 3 | 2 | 3 | 1
Dehydration | 8 | 3 | 5 | 3 | 6 | 4

Table 12: Adverse Reactions Reported in Patients in the Previously Treated Advanced Colorectal Cancer Clinical Trial (greater than or equal to 5% of all patients but with less than 1% grade 3–4)
Adverse Reaction [Event coded in WHO-ART dictionary] | Oxaliplatin+ FU/LV N=150 | Oxaliplatin N=153 | FU/LV N=142
Adverse Reaction [Event coded in WHO-ART dictionary] | All Grades (%) | All Grades (%) | All Grades (%)
Gastrointestinal
Constipation | 32 | 31 | 23
Dyspepsia | 14 | 7 | 10
Taste Perversion | 13 | 5 | 1
Mucositis | 7 | 2 | 10
Flatulence | 5 | 3 | 6
Constitutional Symptoms/Pain/Ocular/Visual
Headache | 17 | 13 | 8
Arthralgia | 10 | 7 | 10
Epistaxis | 9 | 2 | 1
Abnormal Lacrimation | 7 | 1 | 6
Rigors | 7 | 9 | 6
Allergy/Immunology
Rhinitis | 15 | 6 | 4
Allergic Reaction | 10 | 3 | 1
Rash | 9 | 5 | 5
Neurology
Dizziness | 13 | 7 | 8
Insomnia | 9 | 11 | 4
Dermatology/Skin
Hand-Foot Syndrome | 11 | 1 | 13
Flushing | 10 | 3 | 2
Alopecia [No complete alopecia was reported] | 7 | 3 | 3
Pulmonary
Upper Respiratory Tract Infection | 10 | 7 | 4
Pharyngitis | 9 | 2 | 10
Cardiovascular
Peripheral Edema | 10 | 5 | 11
Hepatic/Metabolic/Laboratory/Renal
Hematuria | 6 | 0 | 4
Dysuria | 6 | 1 | 1

Clinically relevant adverse reactions in greater than or equal to 2% and less than 5% of the patients in the oxaliplatin and fluorouracil/leucovorin combination arm (listed in decreasing order of frequency) were: anxiety, myalgia, erythematous rash, increased sweating, conjunctivitis, weight decrease, dry mouth, rectal hemorrhage, depression, ataxia, ascites, hemorrhoids, muscle weakness, nervousness, tachycardia, abnormal micturition frequency, dry skin, pruritus, hemoptysis, purpura, vaginal hemorrhage, melena, somnolence, pneumonia, proctitis, involuntary muscle contractions, intestinal obstruction, gingivitis, tenesmus, hot flashes, enlarged abdomen, and urinary incontinence.

Table 13: Laboratory-Related Adverse Reactions Occurring in ≥5% of Patients with Previously Treated Advanced Colorectal Cancer
Laboratory-Related Adverse Reaction | Oxaliplatin and FU/LV N=150 |  | Oxaliplatin N=153 |  | FU/LV N=142
Laboratory-Related Adverse Reaction | All Grades (%) | Grades 3–4 (%) | All Grades (%) | Grades 3–4 (%) | All Grades (%) | Grades 3–4 (%)
Hematology
Anemia | 81 | 2 | 64 | 1 | 68 | 2
Leukopenia | 76 | 19 | 13 | 0 | 34 | 1
Neutropenia | 73 | 44 | 7 | 0 | 25 | 5
Thrombocytopenia | 64 | 4 | 30 | 3 | 20 | 0
Hepatic
Increased ALT [Alanine transaminase] | 31 | 0 | 36 | 1 | 28 | 3
Increased AST [Aspartate transaminase] | 47 | 0 | 54 | 4 | 39 | 2
Increased Bilirubin | 13 | 1 | 13 | 5 | 22 | 6

Additional Adverse Reactions

The following adverse reactions were observed across clinical trials.

Intravenous site reactions

Injection site reaction, including redness, swelling, and pain, can occur with oxaliplatin. In some cases, skin necrosis has occurred with extravasation.

PRESPRES occurred in less than 0.1% of patients .

Pulmonary fibrosis and interstitial lung disease

Pulmonary fibrosis, which may be fatal, occurred in less than 1% of patients.

6.2 Postmarketing Experience

The following adverse reactions have been identified during postapproval use of oxaliplatin. Because these reactions are reported voluntarily from a population of uncertain size, it is not always possible to reliably estimate their frequency or establish a causal relationship to drug exposure.

- General: angioedema, anaphylactic shock
- Cardiovascular: QT prolongation leading to ventricular arrhythmias, including fatal torsade de pointes; bradyarrhythmia
- Neurological: loss of deep tendon reflexes, dysarthria, Lhermitte's sign, cranial nerve palsies, fasciculations, convulsion
- Hearing and vestibular system: deafness
- Infections: septic shock, including fatal outcomes
- Infusion-related reactions and hypersensitivity reactions: laryngospasm
- Hepatic and gastrointestinal: severe diarrhea/vomiting resulting in hypokalemia, colitis (including Clostridium difficilediarrhea), metabolic acidosis, ileus, intestinal obstruction, pancreatitis, sinusoidal obstruction syndrome, perisinusoidal fibrosis which rarely may progress, focal nodular hyperplasia, esophagitis
- Musculoskeletal and connective tissue: rhabdomyolysis, including fatal outcomes
- Platelet, bleeding, and clotting disorders: immuno-allergic thrombocytopenia, prolonged prothrombin time and INR in patients receiving anticoagulants
- Blood disorders: secondary leukemia
- Red blood cell: hemolytic uremic syndrome, immuno-allergic hemolytic anemia
- Renal: acute tubular necrosis, acute interstitial nephritis, acute renal failure
- Respiratory: interstitial lung diseases (sometimes fatal) and pneumonia (including fatal outcomes)
- Vision: decrease of visual acuity, visual field disturbance, optic neuritis and transient vision loss (reversible following treatment discontinuation)
- Injury, poisoning, and procedural complications: fall-related injuries

7 DRUG INTERACTIONS

7.1 Drugs that Prolong the QT Interval

QT interval prolongation and ventricular arrhythmias can occur with oxaliplatin [see Warnings and Precautions (5.7)] . Avoid coadministration of oxaliplatin with medicinal products with a known potential to prolong the QT interval.

7.2 Use with Nephrotoxic Products

Because platinum-containing species are eliminated primarily through the kidney, clearance of these products may be decreased by coadministration of potentially nephrotoxic compounds [see Clinical Pharmacology (12.3)] . Avoid coadministration of oxaliplatin with medicinal products known to cause nephrotoxicity.

7.3 Use with Anticoagulants

Prolonged prothrombin time and INR occasionally associated with hemorrhage have been reported in patients who received oxaliplatin with fluorouracil/leucovorin while on anticoagulants [see Warnings and Precautions (5.9), Adverse Reactions (6.2)] . Increase frequency of monitoring in patients who are receiving oxaliplatin with fluorouracil/leucovorin and oral anticoagulants.

8 USE IN SPECIFIC POPULATIONS

8.1 Pregnancy

Risk Summary

Based on its direct interaction with DNA, oxaliplatin can cause fetal harm when administered to a pregnant woman. The available human data do not establish the presence or absence of major birth defects or miscarriage related to the use of oxaliplatin. Reproductive toxicity studies demonstrated adverse effects on embryo-fetal development in rats at maternal doses that were below the recommended human dose based on body surface area (see Data) . Advise a pregnant woman of the potential risk to a fetus.

In the U.S. general population, the estimated background risk of major birth defects and miscarriage in clinically recognized pregnancies is 2% to 4% and 15% to 20%, respectively.

Data

Animal data

Pregnant rats were administered oxaliplatin at less than one-tenth the recommended human dose based on body surface area during gestation days (GD)1–5 (preimplantation), GD 6–10, or GD 11–16 (during organogenesis). Oxaliplatin caused developmental mortality (increased early resorptions) when administered on days GD 6–10 and GD 11–16 and adversely affected fetal growth (decreased fetal weight, delayed ossification) when administered on days GD 6–10.

8.2 Lactation

Risk Summary

There are no data on the presence of oxaliplatin or its metabolites in human or animal milk or its effects on the breastfed infant or on milk production. Because of the potential for serious adverse reactions in breastfed infants, advise women not to breastfeed during treatment with oxaliplatin and for 3 months after the final dose.

8.3 Females and Males of Reproductive Potential

Pregnancy Testing

Verify pregnancy status in females of reproductive potential prior to initiating oxaliplatin [see Use in Specific Populations (8.1)] .

Contraception

Oxaliplatin can cause embryo-fetal harm when administered to a pregnant woman [see Use in Specific Populations (8.1)] .

Females

Advise female patients of reproductive potential to use effective contraception while receiving oxaliplatin and for 9 months after the final dose.

Males

Based on its mechanism action as a genotoxic drug, advise males with female partners of reproductive potential to use effective contraception while receiving oxaliplatin and for 6 months after the final dose [see Nonclinical Toxicology (13.1)] .

Infertility

Based on animal studies, oxaliplatin may impair fertility in males and females [see Nonclinical Toxicology (13.1)] .

8.4 Pediatric Use

The safety and effectiveness of oxaliplatin in pediatrics have not been established. Safety and effectiveness were assessed across 4 open-label studies in 235 patients aged 7 months to 22 years with solid tumors.

In a multicenter, open-label, non-comparative, non-randomized study (ARD5531), oxaliplatin was administered to 43 patients with refractory or relapsed malignant solid tumors, mainly neuroblastoma and osteosarcoma. The dose limiting toxicity (DLT) was sensory neuropathy at a dose of 110 mg/m^2. The main adverse reactions were: paresthesia (60%, grade 3–4: 7%), fever (40%, grade 3–4: 7%), and thrombocytopenia (40%, grade 3–4: 27%). No responses were observed.

In an open-label non-randomized study (DFI7434), oxaliplatin was administered to 26 pediatric patients with metastatic or unresectable solid tumors, mainly neuroblastoma and ganglioneuroblastoma. The DLT was sensory neuropathy at a dose of 160 mg/m^2. No responses were observed.

In an open-label, single-agent study (ARD5021), oxaliplatin was administered to 43 pediatric patients with recurrent or refractory embryonal CNS tumors. The most common adverse reactions reported were: leukopenia (67%, grade 3–4: 12%), anemia (65%, grade 3–4: 5%), thrombocytopenia (65%, grade 3–4: 26%), vomiting (65%, grade 3–4: 7%), neutropenia (58%, grade 3–4: 16%), and sensory neuropathy (40%, grade 3–4: 5%).

In an open-label single-agent study (ARD5530), oxaliplatin was administered to 123 pediatric patients with recurrent solid tumors, including neuroblastoma, osteosarcoma, Ewing sarcoma or peripheral PNET, ependymoma, rhabdomyosarcoma, hepatoblastoma, high grade astrocytoma, brain stem glioma, low grade astrocytoma, malignant germ cell tumor and other tumors. The most common adverse reactions reported were: sensory neuropathy (52%, grade 3–4: 12%), thrombocytopenia (37%, grade 3–4: 17%), anemia (37%, grade 3–4: 9%), vomiting (26%, grade 3–4: 4%), increased ALT (24%, grade 3–4: 6%), increased AST (24%, grade 3–4: 2%), and nausea (23%, grade 3–4: 3%).

The pharmacokinetic parameters of ultrafiltrable platinum were evaluated in 105 pediatric patients during the first cycle. The mean clearance in pediatric patients estimated by the population pharmacokinetic analysis was 4.7 L/h (%CV, 41%). Mean platinum pharmacokinetic parameters in ultrafiltrate were Cmaxof 0.75 ± 0.24 mcg/mL, AUC0–48hof 7.52 ± 5.07 mcg∙h/mL and AUCinfof 8.83 ± 1.57 mcg∙h/mL at 85 mg/m^2of oxaliplatin and Cmaxof 1.10 ± 0.43 mcg/mL, AUC0–48hof 9.74 ± 2.52 mcg∙h/mL and AUCinfof 17.3 ± 5.34 mcg∙h/mL at 130 mg/m^2of oxaliplatin.

8.5 Geriatric Use

In the adjuvant treatment trial [see Clinical Studies (14.1)] , 400 patients who received oxaliplatin with fluorouracil/leucovorin were greater than or equal to 65 years. The effect of oxaliplatin in patients greater than or equal to 65 years was not conclusive. Patients greater than or equal to 65 years receiving oxaliplatin experienced more diarrhea and grade 3–4 neutropenia (45% vs 39%) compared to patients less than 65 years.

In the previously untreated advanced colorectal cancer trial [see Clinical Studies (14.2)] , 99 patients who received oxaliplatin with fluorouracil and leucovorin were greater than or equal to 65 years. The same efficacy improvements in response rate, time to tumor progression, and overall survival were observed in the greater than or equal to 65 years patients as in the overall study population. Adverse reactions were similar in patients less than 65 and greater than or equal to 65 years, but older patients may have been more susceptible to diarrhea, dehydration, hypokalemia, leukopenia, fatigue, and syncope.

In the previously treated advanced colorectal cancer trial [see Clinical Studies (14.3)] , 55 patients who received oxaliplatin with fluorouracil and leucovorin were greater than or equal to 65 years. No overall differences in effectiveness were observed between these patients and younger adults. Adverse reactions were similar in patients less than 65 and greater than or equal to 65 years, but older patients may have been more susceptible to diarrhea, dehydration, hypokalemia, and fatigue.

No significant effect of age on the clearance of ultrafiltrable platinum has been observed [see Clinical Pharmacology (12.3)] .

8.6 Patients with Renal Impairment

The AUC of unbound platinum in plasma ultrafiltrate was increased in patients with renal impairment [see Clinical Pharmacology (12.3)] . No dose reduction is recommended for patients with mild (creatinine clearance 50 to 79 mL/min) or moderate (creatinine clearance 30 to 49 mL/min) renal impairment, calculated by Cockcroft-Gault equation. Reduce the dose of oxaliplatin in patients with severe renal impairment (creatinine clearance less than 30 mL/min) [see Dosage and Administration (2.3)].

10 OVERDOSAGE

The maximum dose of oxaliplatin that has been administered in a single infusion is 825 mg. Several cases of overdoses have been reported with oxaliplatin. Adverse reactions observed following an overdosage were grade 4 thrombocytopenia (less than 25,000/mm^3) without bleeding, anemia, sensory neuropathy (including paresthesia, dysesthesia, laryngospasm and facial muscle spasms), gastrointestinal disorders (including nausea, vomiting, stomatitis, flatulence, abdomen enlarged and grade 4 intestinal obstruction), grade 4 dehydration, dyspnea, wheezing, chest pain, respiratory failure, severe bradycardia, and death.

Closely monitor patients suspected of receiving an overdose, including for the adverse reactions described above and administer appropriate supportive treatment.

11 DESCRIPTION

Oxaliplatin is a platinum-based drug with the molecular formula C8H14N2O4Pt and the chemical name of cis-[(1 R,2 R)-1,2-cyclohexanediamine- N, N′][oxalato(2-)- O, O′]platinum. Oxaliplatin is an organoplatinum complex in which the platinum atom is complexed with 1,2-diaminocyclohexane (DACH) and with an oxalate ligand as a leaving group.

The molecular weight is 397.3. Oxaliplatin is slightly soluble in water at 6 mg/mL, very slightly soluble in methanol, and practically insoluble in ethanol and acetone.

Oxaliplatin Injection, for intravenous use, is supplied in vials containing 50 mg or 100 mg of oxaliplatin as a sterile, preservative-free, aqueous solution at a concentration of 5 mg/mL. Water for Injection, USP is present as an inactive ingredient.

12 CLINICAL PHARMACOLOGY

12.1 Mechanism of Action

Oxaliplatin undergoes nonenzymatic conversion in physiologic solutions to active derivatives via displacement of the labile oxalate ligand. Several transient reactive species are formed, including monoaquo and diaquo DACH platinum, which covalently bind with macromolecules. Both inter- and intrastrand Pt-DNA crosslinks are formed. Crosslinks are formed between the N7positions of two adjacent guanines (GG), adjacent adenine-guanines (AG), and guanines separated by an intervening nucleotide (GNG). These crosslinks inhibit DNA replication and transcription. Cytotoxicity is cell-cycle nonspecific.

In vivo studies have shown antitumor activity of oxaliplatin against colon carcinoma. In combination with fluorouracil, oxaliplatin exhibits in vitro and in vivo antiproliferative activity greater than either compound alone in several tumor models (HT29 [colon], GR [mammary], and L1210 [leukemia]).

12.2 Pharmacodynamics

A pharmacodynamic relationship between platinum ultrafiltrate levels and clinical safety and effectiveness has not been established.

12.3 Pharmacokinetics

The reactive oxaliplatin derivatives are present as a fraction of the unbound platinum in plasma ultrafiltrate. After a single 2-hour intravenous infusion of oxaliplatin at a dose of 85 mg/m^2, pharmacokinetic parameters expressed as ultrafiltrable platinum were Cmaxof 0.814 mcg/mL and volume of distribution of 440 L.

Interpatient and intrapatient variability in ultrafiltrable platinum exposure (AUC0–48hr) assessed over 3 cycles was 23% and 6%, respectively.

Distribution

At the end of a 2-hour infusion of oxaliplatin, approximately 15% of the administered platinum is present in the systemic circulation. The remaining 85% is rapidly distributed into tissues or eliminated in the urine. The decline of ultrafiltrable platinum levels following oxaliplatin administration is triphasic, including two distribution phases (t1/2α; 0.43 hours and t1/2β; 16.8 hours).

In patients, plasma protein binding of platinum is irreversible and is greater than 90%. The main binding proteins are albumin and gamma-globulins.

Platinum also binds irreversibly and accumulates (approximately 2-fold) in erythrocytes, where it appears to have no relevant activity. No platinum accumulation was observed in plasma ultrafiltrate following 85 mg/m^2every two weeks.

Elimination

The decline of ultrafiltrable platinum concentrations from plasma is characterized by a long terminal elimination phase (t1/2γ; 391 hours).

Metabolism

Oxaliplatin undergoes rapid and extensive nonenzymatic biotransformation. There is no evidence of cytochrome P450-mediated metabolism in vitro.

Up to 17 platinum-containing derivatives have been observed in plasma ultrafiltrate samples from patients, including several cytotoxic species (monochloro DACH platinum, dichloro DACH platinum, and monoaquo and diaquo DACH platinum) and a number of noncytotoxic, conjugated species.

Excretion

The major route of platinum elimination is renal excretion. At five days after a single 2-hour infusion of oxaliplatin, urinary elimination accounted for about 54% of the platinum eliminated, with fecal excretion accounting for only about 2%. Platinum was cleared from plasma at a rate (10–17 L/h) that was similar to or exceeded the average human glomerular filtration rate (GFR; 7.5 L/h). The renal clearance of ultrafiltrable platinum is significantly correlated with GFR.

Special Populations

Sex

There was no significant effect of sex on the clearance of ultrafiltrable platinum.

Patients with renal impairment

Patients with normal function (CLcr greater than 80 mL/min) and patients with mild (CLcr=50–80 mL/min) and moderate (CLcr equal to 30–49 mL/min) renal impairment received oxaliplatin 85 mg/m^2and those with severe (CLcr less than 30 mL/min) renal impairment received oxaliplatin 65 mg/m^2. Mean dose adjusted AUC of unbound platinum was 40%, 95%, and 342% higher for patients with mild, moderate, and severe renal impairment, respectively, compared to patients with normal renal function. Mean dose adjusted Cmaxof unbound platinum appeared to be similar among the normal, mild and moderate renal function groups, but was 38% higher in the severe group than in the normal group [see Dosage and Administration (2.3)] .

Drug Interaction Studies

No pharmacokinetic interaction between oxaliplatin 85 mg/m^2and infusional fluorouracil has been observed in patients treated every 2 weeks, but increases of fluorouracil plasma concentrations by approximately 20% have been observed with doses of 130 mg/m^2of oxaliplatin administered every 3 weeks.

In vitro platinum was not displaced from plasma proteins by the following medications: erythromycin, salicylate, sodium valproate, granisetron, and paclitaxel.

In vitro oxaliplatin does not inhibit human cytochrome P450 isoenzymes.

13 NONCLINICAL TOXICOLOGY

13.1 Carcinogenesis, Mutagenesis, Impairment of Fertility

Long-term animal studies have not been performed to evaluate the carcinogenic potential of oxaliplatin. Oxaliplatin was not mutagenic to bacteria (Ames test) but was mutagenic to mammalian cells in vitro (L5178Y mouse lymphoma assay). Oxaliplatin was clastogenic both in vitro (chromosome aberration in human lymphocytes) and in vivo (mouse bone marrow micronucleus assay).

In a fertility study, male rats were given oxaliplatin at 0, 0.5, 1, or 2 mg/kg/day for five days every 21 days for a total of three cycles prior to mating with females that received two cycles of oxaliplatin on the same schedule. A dose of 2 mg/kg/day (less than one-seventh the recommended human dose on a body surface area basis) did not affect pregnancy rate, but resulted in 97% postimplantation loss (increased early resorptions, decreased live fetuses, decreased live births), and delayed growth (decreased fetal weight).

Testicular damage, characterized by degeneration, hypoplasia, and atrophy, was observed in dogs administered oxaliplatin at 0.75 mg/kg/day (approximately one-sixth of the recommended human dose on a body surface area basis) × 5 days every 28 days for three cycles. A no effect level was not identified.

14 CLINICAL STUDIES

14.1 Adjuvant Treatment with Oxaliplatin in Combination with Fluorouracil and Leucovorin

The efficacy of oxaliplatin in combination with fluorouracil (FU)/leucovorin (LV) was evaluated in an international, multicenter, randomized (1:1) trial (The Multicenter International Study of Oxaliplatin/5-Fluorouracil/Leucovorin in the Adjuvant Treatment of Colon Cancer [MOSAIC], NCT00275210) in patients with stage II (Dukes' B2) or III (Dukes' C) colon cancer who had undergone complete resection of the primary tumor. Patients were randomized to receive oxaliplatin with fluorouracil/leucovorin or fluorouracil/leucovorin alone for a total of 6 months (i.e., 12 cycles). Table 14 shows the dosing regimens for the two arms.

Eligible patients were between 18 and 75 years of age, had histologically proven stage II (T3–T4N0 M0; Dukes' B2) or III (any T N1–2M0; Dukes' C) colon carcinoma (with the inferior pole of the tumor above the peritoneal reflection, i.e., greater than or equal to 15 cm from the anal margin) and had undergone (within 7 weeks prior to randomization) complete resection of the primary tumor without gross or microscopic evidence of residual disease and carcino-embyrogenic antigen (CEA) less than 10 ng/mL. Additional eligibility criteria were no prior chemotherapy, immunotherapy or radiotherapy; Eastern Cooperative Oncology Group performance status of 0, 1, or 2 (Karnofsky Performance Status greater than or equal to 60%); no pre-existing neuropathy; and absolute neutrophil count (ANC) greater than or equal to 1.5 × 10^9/L, platelets greater than or equal to 100 × 10^9/L, serum creatinine less than or equal to 1.25 × upper limit normal (ULN), total bilirubin less than 2 × ULN, and aspartate transaminase (AST)/alanine transaminase (ALT) less than 2 × ULN. The major efficacy outcome was 3-year disease-free survival (DFS).

Table 14: Dosing Regimens in Adjuvant Treatment Study
Treatment Arm | Dose | Regimen
Oxaliplatin + FU/LV (FOLFOX4) (N=1123) | Day 1: Oxaliplatin: 85 mg/m^2(2-hour infusion) + LV: 200 mg/m^2(2-hour infusion), followed by FU: 400 mg/m^2(bolus), 600 mg/m^2(22-hour infusion) Day 2: LV: 200 mg/m^2(2-hour infusion), followed by FU: 400 mg/m^2(bolus), 600 mg/m^2(22-hour infusion) | every 2 weeks 12 cycles
FU/LV (N=1123) | Day 1: LV: 200 mg/m^2(2-hour infusion), followed by FU: 400 mg/m^2(bolus), 600 mg/m^2(22-hour infusion) Day 2: LV: 200 mg/m^2(2-hour infusion), followed by FU: 400 mg/m^2(bolus), 600 mg/m^2(22-hour infusion) | every 2 weeks 12 cycles

There were 2246 patients enrolled, of whom 1347 (60%) had Stage III disease. Tables 15 and 16 show the baseline characteristics and exposure to oxaliplatin.

Table 15: Baseline Characteristics in Adjuvant Treatment Study
 | Oxaliplatin + Infusional FU/LV N=1123 | Infusional FU/LV N=1123
Sex: Male (%) | 56.1 | 52.4
Female (%) | 43.9 | 47.6
Median age (years) | 61.0 | 60.0
<65 years of age (%) | 64.4 | 66.2
≥65 years of age (%) | 35.6 | 33.8
KPS (%)
100 | 29.7 | 30.5
90 | 52.2 | 53.9
80 | 4.4 | 3.3
70 | 13.2 | 11.9
≤60 | 0.6 | 0.4
Primary site (%)
Colon including cecum | 54.6 | 54.4
Sigmoid | 31.9 | 33.8
Recto sigmoid | 12.9 | 10.9
Other including rectum | 0.6 | 0.9
Bowel obstruction (%)
Yes | 17.9 | 19.3
Perforation (%)
Yes | 6.9 | 6.9
Stage at Randomization (%)
II (T=3,4 N=0, M=0) | 40.1 | 39.9
III (T=any, N=1,2, M=0) | 59.6 | 59.3
IV (T=any, N=any, M=1) | 0.4 | 0.8
Staging – T (%)
T1 | 0.5 | 0.7
T2 | 4.5 | 4.8
T3 | 76.0 | 75.9
T4 | 19.0 | 18.5
Staging – N (%)
N0 | 40.2 | 39.9
N1 | 39.4 | 39.4
N2 | 20.4 | 20.7
Staging – M (%)
M1 | 0.4 | 0.8

Table 16: Exposure to Oxaliplatin in Adjuvant Treatment Study
 | Oxaliplatin + Infusional FU/LV N=1108 | Infusional FU/LV N=1111
Median Relative Dose Intensity (%)
FU | 84.4 | 97.7
Oxaliplatin | 80.5 | N/A
Median Number of Cycles | 12 | 12
Median Number of Cycles with oxaliplatin | 11 | N/A

The median duration of follow-up was approximately 77 months. In the overall and the stage III colon cancer populations, DFS was statistically significantly improved in the oxaliplatin-containing arm compared to fluorouracil/leucovorin alone; however, a statistically significant improvement in DFS was not observed in Stage II patients. No significant differences in overall survival (OS) were detected in the overall population or those with Stage III disease. Table 17 and Figures 1 and 2 summarize the 5-year DFS rates in the overall randomized population and in patients with stage II and III disease based on an intention-to-treat (ITT) analysis.

Table 17: Summary of DFS Analysis in Adjuvant Treatment Study – ITT Population
Parameter | Oxaliplatin + Infusional FU/LV | Infusional FU/LV
Overall
Number of patients | 1123 | 1123
Number of events – relapse or death (%) | 304 (27.1) | 360 (32.1)
5-yr Disease-free survival % (95% CI) | 73.3 (70.7, 76.0) | 67.4 (64.6, 70.2)
Hazard ratio (95% CI) | 0.80 (0.68, 0.93)
Stratified Log rank test | p=0.003
Stage III (Dukes' C)
Number of patients | 672 | 675
Number of events – relapse or death (%) | 226 (33.6) | 271 (40.1)
5-yr Disease-free survival % (95% CI) | 66.4 (62.7, 70.0) | 58.9 (55.2, 62.7)
Hazard ratio (95% CI) | 0.78 (0.65, 0.93)
Log rank test | p=0.005
Stage II (Dukes' B2)
Number of patients | 451 | 448
Number of events – relapse or death (%) | 78 (17.3) | 89 (19.9)
5-yr Disease-free survival % (95% CI) | 83.7 (80.2, 87.1) | 79.9 (76.2, 83.7)
Hazard ratio (95% CI) | 0.84 (0.62, 1.14)
Log rank test | p=0.258
A hazard ratio of less than 1 favors oxaliplatin + Infusional FU/LV
Data cut off for disease-free survival June 1, 2006

Figure 1: Kaplan-Meier Curves of Disease-Free Survival (cutoff: 1 June 2006) in Adjuvant Treatment Trial – ITT Population

Figure 2: Kaplan-Meier Curves of Disease-Free Survival in Stage III Patients (cutoff: 1 June 2006) in Adjuvant Treatment Trial – ITT Population

Table 18 summarizes the OS results in the overall randomized population and in patients with stage II and III disease, based on the ITT analysis.

Table 18: Summary of OS Analysis in Adjuvant Treatment – ITT Population
Parameter | Oxaliplatin + Infusional FU/LV | Infusional FU/LV
Overall
Number of patients | 1123 | 1123
Number of death events (%) | 245 (21.8) | 283 (25.2)
Hazard ratio (95% CI) | 0.84 (0.71 , 1.00)
Stage III (Dukes' C)
Number of patients | 672 | 675
Number of death events (%) | 182 (27.1) | 220 (32.6)
Hazard ratio (95% CI) | 0.80 (0.65 , 0.97)
Stage II (Dukes' B2)
Number of patients | 451 | 448
Number of death events (%) | 63 (14.0) | 63 (14.1)
Hazard ratio (95% CI) | 1.00 (0.70, 1.41)
A hazard ratio of less than 1 favors oxaliplatin + Infusional FU/LV
Data cut off for overall survival January 16, 2007

14.2 Previously Untreated Advanced Colorectal Cancer

The efficacy of oxaliplatin in combination with fluorouracil (FU)/leucovorin (LV) was evaluated in a North American, multicenter, open-label, randomized, active-controlled trial (A Randomized Phase III Trial of Three Different Regimens of CPT-11 Plus 5-Fluorouracil and Leucovorin Compared to 5-Fluorouracil and Leucovorin in Patients with Advanced Adenocarcinoma of the Colon and Rectum; NCT00003594). The trial included 7 arms at different times during its conduct, four of which were closed due to either changes in the standard of care, toxicity, or simplification. During the trial, the control arm was changed to irinotecan with fluorouracil/leucovorin.

The results reported below compared the efficacy of oxaliplatin with fluorouracil/leucovorin and oxaliplatin with irinotecan to an approved control regimen of irinotecan with fluorouracil/leucovorin in 795 concurrently randomized patients previously untreated for locally advanced or metastatic colorectal cancer. Table 19 presents the dosing regimens for the three arms. After completion of enrollment, the dose of irinotecan with fluorouracil/leucovorin was decreased due to toxicity.

Eligible patients were at least 18 years of age; had known locally advanced, locally recurrent, or metastatic colorectal adenocarcinoma not curable by surgery or amenable to radiation therapy; with an Eastern Cooperative Oncology Group (ECOG) performance status ≤0, 1, or 2. Patients had to have absolute neutrophil count (ANC) greater than or equal to 1.5 × 10^9/L, platelets greater than or equal to 100 × 10^9/L, hemoglobin greater than or equal to 9.0 g/dL, creatinine less than or equal to 1.5 × upper limit of normal (ULN), total bilirubin less than or equal to 1.5 mg/dL, aspartate transaminase (AST) less than or equal to 5 × ULN, and alkaline phosphatase less than or equal to 5 × ULN. Patients may have received adjuvant treatment for resected Stage II or III disease without recurrence within 12 months. Randomization was stratified by ECOG performance status (0, 1 vs 2), prior adjuvant chemotherapy (yes vs no), prior immunotherapy (yes vs no), and age (less than 65 vs greater than or equal to 65 years). Although no post study treatment was specified in the protocol, 65% to 72% of patients received additional post study chemotherapy after study treatment discontinuation on all arms. Fifty-eight percent of patients on the oxaliplatin with fluorouracil/leucovorin arm received an irinotecan-containing regimen and 23% of patients on the irinotecan with fluorouracil/leucovorin arm received an oxaliplatin-containing regimen. The main efficacy outcome measure was 3-year disease-free survival (DFS) and additional efficacy outcome measures were overall survival (OS).

Table 19: Dosing Regimens for Previously Untreated Advanced Colorectal Cancer Clinical Trial
Treatment Arm | Dose | Regimen
Oxaliplatin + FU/LV (FOLFOX4) (N=267) | Day 1: Oxaliplatin: 85 mg/m^2(2-hour infusion) + LV 200 mg/m^2(2-hour infusion), followed by FU: 400 mg/m^2(bolus), 600 mg/m^2(22-hour infusion) Day 2: LV 200 mg/m^2(2-hour infusion), followed by FU: 400 mg/m^2(bolus), 600 mg/m^2(22-hour infusion) | every 2 weeks
Irinotecan + FU/LV (IFL) (N=264) | Day 1: irinotecan 125 mg/m^2as a 90-min infusion + LV 20 mg/m^2as a 15-min infusion or intravenous push, followed by FU 500 mg/m^2intravenous bolus weekly × 4 | every 6 weeks
Oxaliplatin + Irinotecan (IROX) (N=264) | Day 1: Oxaliplatin: 85 mg/m^2intravenous (2-hour infusion) + irinotecan 200 mg/m^2intravenous over 30 minutes | every 3 weeks

Table 20 presents the baseline characteristics.

Table 20: Baseline Characteristics for Previously Untreated Advanced Colorectal Cancer Clinical Trial
 | Oxaliplatin + FU/LV N=267 | Irinotecan + FU/LV N=264 | Oxaliplatin + Irinotecan N=264
Sex: Male (%) | 58.8 | 65.2 | 61.0
Female (%) | 41.2 | 34.8 | 39.0
Median age (years) | 61.0 | 61.0 | 61.0
<65 years of age (%) | 61 | 62 | 63
≥65 years of age (%) | 39 | 38 | 37
ECOG (%)
0–1 | 94.4 | 95.5 | 94.7
2 | 5.6 | 4.5 | 5.3
Involved organs (%)
Colon only | 0.7 | 0.8 | 0.4
Liver only | 39.3 | 44.3 | 39.0
Liver + other | 41.2 | 38.6 | 40.9
Lung only | 6.4 | 3.8 | 5.3
Other (including lymph nodes) | 11.6 | 11.0 | 12.9
Not reported | 0.7 | 1.5 | 1.5
Prior radiation (%) | 3.0 | 1.5 | 3.0
Prior surgery (%) | 74.5 | 79.2 | 81.8
Prior adjuvant (%) | 15.7 | 14.8 | 15.2

The median number of cycles administered per patient was 10 (23.9 weeks) for the oxaliplatin plus fluorouracil/leucovorin regimen, 4 (23.6 weeks) for the irinotecan plus fluorouracil/leucovorin regimen, and 7 (21.0 weeks) for the oxaliplatin plus irinotecan regimen.

Patients who received oxaliplatin with fluorouracil/leucovorin had a significantly longer time to tumor progression based on investigator assessment, longer OS, and a significantly higher confirmed response rate based on investigator assessment compared to patients who received irinotecan with fluorouracil/leucovorin. Efficacy results are summarized in Table 21 and Figure 3.

Table 21: Efficacy Results for Previously Untreated Advanced Colorectal Cancer Trial
 | Oxaliplatin + FU/LV N=267 | Irinotecan + FU/LV N=264 | Oxaliplatin + Irinotecan N=264
Survival (ITT)
Number of deaths (%) | 155 (58.1) | 192 (72.7) | 175 (66.3)
Median survival (months) | 19.4 | 14.6 | 17.6
Hazard ratio (95% CI) [A hazard ratio of less than 1 favors ELOXATIN + Infusional FU/LV] | 0.65 (0.53, 0.80) [Compared to irinotecan plus fluorouracil/leucovorin (IFL) arm] |  | -
P-value | <0.0001 |  | -
TTP (ITT, investigator assessment)
Percentage of progressors | 82.8 | 81.8 | 89.4
Median TTP (months) | 8.7 | 6.9 | 6.5
Hazard ratio (95% CI) | 0.74 (0.61, 0.89) |  | -
P-value | 0.0014 |  | -
Response Rate (investigator assessment) [Based on all patients with measurable disease at baseline]
Patients with measurable disease | 210 | 212 | 215
Complete response, N (%) | 13 (6.2) | 5 (2.4) | 7 (3.3)
Partial response, N (%) | 82 (39.0) | 64 (30.2) | 67 (31.2)
Complete and partial response, N (%) | 95 (45.2) | 69 (32.5) | 74 (34.4)
95% CI | (38.5, 52.0) | (26.2, 38.9) | (28.1, 40.8)
P-value | 0.0080 |  | -
The numbers in the response rate and TTP analysis are based on unblinded investigator assessment.

Figure 3: Kaplan-Meier Curves for Overall Survival in Previously Untreated Advanced Colorectal Cancer Trial

In descriptive subgroup analyses, the improvement in overall survival (OS) for oxaliplatin with fluorouracil/leucovorin compared to irinotecan with fluorouracil/leucovorin appeared to be maintained across age groups, prior adjuvant treatment, number of organs involved and both sexes; however, the effect appeared larger among women than men.

14.3 Previously Treated Advanced Colorectal Cancer

The efficacy of oxaliplatin in combination with fluorouracil (FU)/leucovorin (LV) was evaluated in a multicenter, open-label, randomized, three-arm controlled trial was conducted in the US and Canada in patients with advanced colorectal cancer who had relapsed/progressed during or within 6 months of first-line treatment with bolus fluorouracil/leucovorin and irinotecan (A multicenter, open-label, randomized, three-arm study of 5-fluorouracil (5-FU) + leucovorin (LV) or oxaliplatin or a combination of 5-FU/LV + oxaliplatin as second-line treatment of metastatic colorectal carcinoma: NCT00008281). Patients were randomized to one of three regimens; the dosing regimens are presented in Table 22. Eligible patients were at least 18 years of age, had unresectable, measurable, histologically proven colorectal adenocarcinoma, with a Karnofsky performance status (KPS) greater than 50%. Patients had to have aspartate transaminase (AST), alanine transaminase (ALT) and alkaline phosphatase less than or equal to 2× upper limit of normal (ULN), unless liver metastases were present and documented at baseline by CT or MRI scan, in which case less than or equal to 5× ULN was permitted. Prior radiotherapy was permitted if it had been completed at least 3 weeks before randomization. The main efficacy outcome measure was 3-year disease-free survival (DFS) and an additional outcome measure was overall survival (OS).

Table 22: Dosing Regimens in Refractory and Relapsed Colorectal Cancer Trial
Treatment Arm | Dose | Regimen
Oxaliplatin + FU/LV (N=152) | Day 1: Oxaliplatin: 85 mg/m^2(2-hour infusion) + LV 200 mg/m^2(2-hour infusion), followed by FU: 400 mg/m^2(bolus), 600 mg/m^2(22-hour infusion) Day 2: LV 200 mg/m^2(2-hour infusion), followed by FU: 400 mg/m^2(bolus), 600 mg/m^2(22-hour infusion) | every 2 weeks
FU/LV (N=151) | Day 1: LV 200 mg/m^2(2-hour infusion), followed by FU: 400 mg/m^2(bolus), 600 mg/m^2(22-hour infusion) Day 2: LV 200 mg/m^2(2-hour infusion), followed by FU: 400 mg/m^2(bolus), 600 mg/m^2(22-hour infusion) | every 2 weeks
Oxaliplatin (N=156) | Day 1: Oxaliplatin 85 mg/m^2(2-hour infusion) | every 2 weeks

Patients must have had at least one unidimensional lesion measuring greater than or equal to 20 mm using conventional CT or MRI scans or greater than or equal to 10 mm using a spiral CT scan. Tumor response and progression were assessed every 3 cycles (6 weeks) using the Response Evaluation Criteria in Solid Tumors (RECIST) until radiological documentation of progression or for 13 months following the first dose of study drug(s), whichever came first. Confirmed responses were based on two tumor assessments separated by at least 4 weeks. Baseline characteristics are shown in Table 23.

Table 23: Baseline Characteristics in Refractory and Relapsed Colorectal Cancer Trial
 | Oxaliplatin + FU/LV N=152 | Oxaliplatin N=156 | FU/LV N=151
Sex: Male (%) | 57.2 | 60.9 | 54.3
Female (%) | 42.8 | 39.1 | 45.7
Median age (years) | 59.0 | 61.0 | 60.0
Range | 22–88 | 27–79 | 21–80
Race (%)
Caucasian | 88.8 | 84.6 | 87.4
Black | 5.9 | 7.1 | 7.9
Asian | 2.6 | 2.6 | 1.3
Other | 2.6 | 5.8 | 3.3
KPS (%)
70–100 | 95.4 | 92.3 | 94.7
50–60 | 2.0 | 4.5 | 2.6
Not reported | 2.6 | 3.2 | 2.6
Prior radiotherapy (%) | 25.0 | 19.2 | 25.2
Prior pelvic radiation (%) | 21.1 | 13.5 | 18.5
Number of metastatic sites (%)
1 | 25.7 | 31.4 | 27.2
≥2 | 74.3 | 67.9 | 72.2
Liver involvement (%)
Liver only | 18.4 | 25.6 | 22.5
Liver + other | 53.3 | 59.0 | 60.3

The median number of cycles administered per patient was 6 for the oxaliplatin and fluorouracil/leucovorin combination and 3 each for fluorouracil/leucovorin alone and oxaliplatin alone. Patients treated with the combination of oxaliplatin and fluorouracil/leucovorin had an increased response rate compared to patients given fluorouracil/leucovorin or oxaliplatin alone. Efficacy results are summarized in Tables 24 and 25.

Table 24: Response Rates in Refractory and Relapsed Colorectal Cancer Clinical Trial – ITT Analysis
Best Response | Oxaliplatin + FU/LV N=152 | Oxaliplatin N=156 | FU/LV N=151
Complete Response | 0 | 0 | 0
Partial Response | 13 (9%) | 2 (1%) | 0
P-value | 0.0002 FU/LV vs Oxaliplatin + FU/LV
95% CI | 4.6%, 14.2% | 0.2%, 4.6% | 0, 2.4%

Table 25: Radiographic Time to Progression (TTP) [This is not an ITT analysis. Events were limited to radiographic disease progression documented by independent review of radiographs. Clinical progression was not included in this analysis, and 18% of patients were excluded from the analysis based on unavailability of the radiographs for independent review.] in Refractory and Relapsed Colorectal Cancer Clinical Trial
Arm | Oxaliplatin + FU/LV N=152 | Oxaliplatin N=156 | FU/LV N=151
Number of progressors | 50 | 101 | 74
Number of patients with no radiological evaluation beyond baseline | 17 (11%) | 16 (10%) | 22 (15%)
Median TTP (months) | 4.6 | 1.6 | 2.7
95% CI | 4.2, 6.1 | 1.4, 2.7 | 1.8, 3.0

At the time of the interim analysis 49% of the radiographic progression events had occurred. In this interim analysis an estimated 2-month increase in median time to radiographic progression was observed compared to fluorouracil/leucovorin alone.

15 REFERENCES

1. "OSHA Hazardous Drugs." OSHA. http://www.osha.gov/SLTC/hazardousdrugs/index.html

16 HOW SUPPLIED/STORAGE AND HANDLING

Oxaliplatin Injection is supplied in clear, glass, single-dose vials with gray elastomeric stoppers and aluminum flip-off seals containing 50 mg or 100 mg of oxaliplatin as a clear, colorless, sterile, preservative-free, aqueous solution at a concentration of 5 mg/mL.

NDC 0955-1731-10: 50 mg single-dose vial with green flip-off seal individually packaged in a carton.

NDC 0955-1733-20: 100 mg single-dose vial with dark blue flip-off seal individually packaged in a carton.

STORAGE AND HANDLING

Store at 25°C (77°F); excursions permitted to 15°C to 30°C (59°F to 86°F). Do not freeze and protect from light (keep in original outer carton). Discard unused portion.

Oxaliplatin is a cytotoxic drug. Follow applicable special handling and disposal procedures.^1The use of gloves is recommended. If a solution of oxaliplatin contacts the skin, wash the skin immediately and thoroughly with soap and water. If oxaliplatin contacts the mucous membranes, flush thoroughly with water.

17 PATIENT COUNSELING INFORMATION

Hypersensitivity Reactions

Advise patients of the potential risk of hypersensitivity and that oxaliplatin is contraindicated in patients with a history of hypersensitivity reactions to oxaliplatin and other platinum-based drugs. Instruct patients to seek immediate medical attention for signs of severe hypersensitivity reaction such as chest tightness; shortness of breath; wheezing; dizziness or faintness; or swelling of the face, eyelids, or lips [see Warnings and Precautions (5.1)].

Peripheral Sensory Neuropathy

Advise patients of the risk of acute reversible or persistent-type neurosensory toxicity. Advise patients to avoid cold drinks, use of ice, and exposure of skin to cold temperature or cold objects [see Warnings and Precautions (5.2)] .

Myelosuppression

Inform patients that oxaliplatin can cause low blood cell counts and the need for frequent monitoring of blood cell counts. Advise patients to contact their healthcare provider immediately for bleeding, fever, particularly if associated with persistent diarrhea, or symptoms of infection develop [see Warnings and Precautions (5.3)] .

Posterior Reversible Encephalopathy Syndrome

Advise patients of the potential effects of vision abnormalities, in particular transient vision loss (reversible following therapy discontinuation), which may affect the patients' ability to drive and use machines [see Warnings and Precautions (5.4)] .

Pulmonary Toxicity

Advise patients to report immediately to their healthcare provider any persistent or recurrent respiratory symptoms, such as non-productive cough and dyspnea [see Warnings and Precautions (5.5)] .

Hepatotoxicity

Advise patients to report signs or symptoms of hepatic toxicity to their healthcare provider [see Warnings and Precautions (5.6)].

QT Interval Prolongation

Advise patients that oxaliplatin can cause QTc interval prolongation and to inform their physician if they have any symptoms, such as syncope [see Warnings and Precautions (5.7)] .

Rhabdomyolysis

Advise patients to contact their healthcare provider immediately for new or worsening signs or symptoms of muscle toxicity, dark urine, decreased urine output, or the inability to urinate [see Warnings and Precautions (5.8)].

Hemorrhage

Advise patients that oxaliplatin may increase the risk of bleeding and to promptly inform their healthcare provider of any bleeding episodes [see Warnings and Precautions (5.9)].

Embryo-Fetal Toxicity

Advise females of reproductive potential of the potential risk to a fetus. Advise females to inform their healthcare provider of a known or suspected pregnancy [see Warnings and Precautions (5.10), Use in Specific Populations (8.1)] .

Advise females of reproductive potential to use effective contraception during treatment with oxaliplatin and for 9 months after the final dose [see Use in Specific Populations (8.3)] .

Advise male patients with female partners of reproductive potential to use effective contraception during treatment with oxaliplatin and for 6 months after the final dose [see Use in Specific Populations (8.3), Nonclinical Toxicology (13.1)] .

Lactation

Advise women not to breastfeed during treatment with oxaliplatin and for 3 months after the final dose [see Use in Specific Populations (8.2)] .

Infertility

Advise females and males of reproductive potential that oxaliplatin may impair fertility [see Use in Specific Populations (8.3), Nonclinical Toxicology (13.1)] .

Gastrointestinal

Advise patients to contact their healthcare provider for persistent vomiting, diarrhea, or signs of dehydration [see Adverse Reactions (6.1)] .

Drug Interactions

Inform patients about the risk of drug interactions and the importance of providing a list of prescription and nonprescription drugs to their healthcare provider [see Drug Interactions (7)] .

Patient Information
Oxaliplatin Injection,
for intravenous use

What is the most important information I should know about oxaliplatin?
Oxaliplatin can cause serious allergic reactions, including allergic reactions that can lead to death. Oxaliplatin is a platinum-based medicine. Serious allergic reactions including death can happen in people who take oxaliplatin and who have had previous allergic reactions to platinum-based medicines. Serious allergic reactions can happen within a few minutes of your oxaliplatin infusion or any time during your treatment with oxaliplatin.
Get emergency help right away if you:

- have trouble breathing
- feel like your throat is closing up
- chest tightness

Call your doctor right away if you have any of the following signs or symptoms of an allergic reaction:

- rash
- flushed face
- hives
- itching
- swelling of your lips or tongue, face or eyelids

- wheezing
- sudden cough
- dizziness or feel faint
- sweating
- chest pain

See " What are the possible side effects of oxaliplatin?" for information about other serious side effects.

What is oxaliplatin?
Oxaliplatin is an anti-cancer (chemotherapy) medicine that is used with other anti-cancer medicines called fluorouracil and leucovorin to treat people with:

- stage III colon cancer after surgery to remove the tumor
- advanced colon or rectal cancer (colorectal cancer)

It is not known if oxaliplatin is safe and effective in children.

Do not receive oxaliplatin ifyou are allergic to oxaliplatin or any of the ingredients in oxaliplatin or if you are allergic to other platinum-based medicines. See the end of this leaflet for a complete list of the ingredients in oxaliplatin.
Ask your doctor if you are not sure if you have taken a platinum-based medicine.

Before receiving oxaliplatin, tell your doctor about all of your medical conditions, including if you:

- have an infection
- have lung, liver, or kidney problems
- have bleeding problems
- have or had heart problems such as an abnormal heart test called an electrocardiogram (ECG or EKG), a condition called long QT syndrome, an irregular or slow heartbeat, or a family history of heart problems
- have had changes in the level of certain blood salt (electrolytes) levels, including potassium, magnesium, and calcium
- are pregnant or plan to become pregnant. Oxaliplatin can harm your unborn baby. Tell your doctor right away if you become pregnant or think you may be pregnant during treatment with oxaliplatin.
  Females who are able to become pregnant:
  - Your doctor will do a pregnancy test before you start treatment with oxaliplatin.
  - You should use effective birth control (contraception) during treatment with oxaliplatin and for 9 months after the final dose. Talk to your doctor about forms of birth control that may be right for you.
  Maleswith female partners who are able to become pregnant should use effective birth control during treatment with oxaliplatin and for 6 months after the final dose.
- are breastfeeding or plan to breastfeed. It is not known if oxaliplatin passes into your breast milk. Do not breastfeed during treatment with oxaliplatin and for 3 months after the final dose.

Tell your doctor about all the medicines you take, including prescription and over-the-counter medicines, vitamins, and herbal supplements.
Know the medicines you take. Keep a list of them and show it to your doctor and pharmacist when you get a new medicine.

How will I receive oxaliplatin?

- Oxaliplatin is given to you into your vein through an intravenous (IV) tube.
- Your doctor will prescribe oxaliplatin in a dose that is right for you.
- Your doctor may change how often you receive oxaliplatin, your dose, or how long your infusion will take.
- You and your doctor will decide how many oxaliplatin treatments you will receive.
- It is very important that you do exactly what your doctor and nurse tell you to do.
- Some medicines may be given to you before oxaliplatin to help prevent nausea and vomiting.
- Each treatment course is given to you over 2 days. You will receive oxaliplatin on the first day only.
- There are usually 14 days (2 weeks) between each chemotherapy treatment course.
- It is important for you to keep all of your medical appointments. Call your doctor if you miss an appointment. There may be special instructions for you.

Treatment Day 1:

- Oxaliplatin and leucovorin will be given through a thin plastic tube into a vein (intravenous infusion or IV) and given for 2 hours. You will be watched by a healthcare provider during this time.
- Right after the oxaliplatin and leucovorin are given, 2 doses of fluorouracil will be given. The first dose is given right away into your IV tube. The second dose will be given into your IV tube over the next 22 hours, using a pump device.

Treatment Day 2:
You will notget oxaliplatin on Day 2. Leucovorin and fluorouracil will be given the same way as on Day 1.
The fluorouracil will be given through your IV with a pump. If you have any problems with the pump or the tube, call your doctor, your nurse, or the person who is responsible for your pump. Do not let anyone other than a healthcare provider touch your infusion pump or tubing.

What should I avoid while receiving oxaliplatin?

- Avoid cold temperatures and cold objects. Cover your skin if you go outdoors in cold temperatures.
- Do not drink cold drinks or use ice cubes in drinks.
- Do not put ice or ice packs on your body.
- Oxaliplatin can cause dizziness, vision problems, or vision loss that can affect your ability to drive or use machines. You should not drive or operate machinery if you develop these symptoms while receiving oxaliplatin.

See " How can I reduce the side effects caused by cold temperatures?" for more information.
Talk with your doctor and nurse about your level of activity during treatment with oxaliplatin. Follow their instructions.

What are the possible side effects of oxaliplatin?
Oxaliplatin can cause serious side effects, including:

- See " What is the most important information I should know about oxaliplatin?"
- Nerve problems.Oxaliplatin can affect how your nerves work and make you feel. Nerve problems may happen with the first treatment or within two days after your treatment with oxaliplatin. Nerve problems may last a short time (acute) or may become persistent. Symptoms may improve after stopping treatment with oxaliplatin. Exposure to cold or cold objects may cause or worsen nerve problems. Tell your doctor right away if you get any signs of nerve problems, including:
  - very sensitive to cold temperatures and cold objects
  - trouble breathing, swallowing, or saying words, jaw tightness, odd feelings in your tongue, or chest pressure
  - pain, tingling, burning (pins and needles, numb feeling) in your hands, feet, or around your mouth or throat, which may cause problems walking, fall and fall-related injuries, or problems performing activities of daily living

For information on ways to lessen or help with nerve problems, see the section " How can I reduce the side effects caused by cold temperatures?" below.

- Severe low blood cell counts (myelosuppression).Oxaliplatin when used with fluorouracil and leucovorin can cause low blood cells counts. Low blood cell counts are common with oxaliplatin when used with fluorouracil and leucovorin and can lead to serious infection and death. Your doctor will do blood tests to check your blood cell counts before starting oxaliplatin and during treatment. Tell your doctor right away if you have a fever greater than 100.9°F (38.3°C) or a prolonged fever greater than 100.4°F (38°C) for more than one hour (febrile neutropenia). Call your doctor right away if you get any of the following signs of infection:

- chills or shivering
- pain on swallowing
- sore throat

- cough that brings up mucus
- burning or pain on urination
- redness or swelling at intravenous site
- persistent diarrhea

- Posterior Reversible Encephalopathy Syndrome (PRES).PRES is a rare condition that affects the brain. Tell your doctor right away if you have any of the following signs and symptoms of PRES:
  - headache
  - confusion or a change in the way you think
  - seizures
  - vision problems, such as blurriness or vision loss
- Lung problems.Oxaliplatin can cause lung problems that may lead to death. Tell your doctor right away if you get any of the following symptoms as these may be indicators of a serious lung disease:

- shortness of breath
- wheezing

- cough

- Liver problems (hepatotoxicity).Your doctor will do blood tests to check your liver when you start receiving oxaliplatin, and before each treatment course as needed.
- Heart problems.Oxaliplatin can cause heart problems that have led to death. Your doctor may do blood and heart tests during treatment with oxaliplatin if you have certain heart problems. If you faint (lose consciousness), or have an irregular heartbeat or chest pain during treatment with oxaliplatin, get medical help right away as this may be a sign of a serious heart condition.
- Muscle problems.Oxaliplatin can cause muscle damage (rhabdomyolysis) which can lead to death. Tell your doctor right away if you have muscle pain and swelling, along with weakness, fever, red-brown urine , decreased amount of urine or trouble urinating.
- Bleeding problems (hemorrhage).Oxaliplatin when used with fluorouracil and leucovorin can cause bleeding problems (hemorrhage) that can lead to death. Your risk of bleeding may increase if you are also taking a blood thinner medicine. Tell your healthcare provider if you have any signs or symptoms of bleeding, including:

- blood in your stools or black stools (looks like tar)
- pink or brown urine
- unexpected bleeding, or bleeding that is severe or you cannot control
- vomit blood or vomit that looks like coffee grounds
- cough up blood or blood clots

- increased bruising
- dizziness
- weakness
- confusion
- changes in speech
- headache that lasts a long time

The most common side effects of oxaliplatin include:

- numbness, pain, tingling, and burning along the nerves
- low white blood cells (blood cells important for fighting infection)
- low platelet count (important for clotting and to control bleeding)
- low red blood cells (blood cells that carry oxygen to the tissues)
- nausea

- changes in liver function tests
- diarrhea
- vomiting
- tiredness
- mouth sores

Oxaliplatin may cause fertility problems in males and females. Tell your doctor if you have any side effect that bothers your or that does not go away. These are not all the possible side effects of oxaliplatin. For more information, ask your doctor or pharmacist.
Call your doctor for medical advice about side effects. You may report side effects to FDA at 1-800-FDA-1088.

How can I reduce the side effects caused by cold temperatures?

- Cover yourself with a blanket while you are getting your oxaliplatin infusion.
- Do not breathe deeply when exposed to cold air.
- Wear warm clothing in cold weather at all times. Cover your mouth and nose with a scarf or a pull-down cap (ski cap) to warm the air that goes to your lungs.
- Wear gloves when taking things from the freezer or refrigerator.
- Drink fluids warm or at room temperature.
- Always drink through a straw.
- Do notuse ice chips if you have nausea or mouth sores. Ask your doctor about what you can use.
- Be aware that most metals are cold to touch, especially in the winter. These include your car door and mailbox. Wear gloves to touch cold objects.
- Do not run the air conditioning at high levels in the house or in the car in hot weather.
- If your body gets cold, warm-up the affected part. If your hands get cold, wash them with warm water.
- Always let your doctor know beforeyour next treatment how well you did since your last visit.

Your doctor may have other useful tips for helping you with side effects.

General information about the safe and effective use of oxaliplatin.
Medicines are sometimes prescribed for purposes other than those listed in the Patient Information leaflet.
You can ask your doctor or pharmacist for information about oxaliplatin that is written for health professionals.

What are the ingredients in oxaliplatin?
Active ingredient: oxaliplatin
Inactive ingredient: water for injection
Manufactured by: Winthrop U.S., a business of sanofi-aventis U.S. LLC, Bridgewater, NJ 08807, A SANOFI COMPANY
PREMIERProRx®is a registered trademark of Premier Healthcare Alliance, L.P., used under license.©2023 sanofi-aventis U.S. LLC

This Patient Information has been approved by the U.S. Food and Drug Administration.

Revised: June 2023

PRINCIPAL DISPLAY PANEL - 10 mL Vial Carton

NDC 0955-1731-10 Rx only

OXALIplatin injection

50 mg / 10 mL
(5 mg/mL)

For Intravenous Infusion After Dilution

Warning: Cytotoxic Agent
See full prescribing information.

DO NOT MIX OR ADD TO
SODIUM CHLORIDE/
CHLORIDE-CONTAINING
SOLUTIONS

One single-dose vial

PREMIERProRx®

PRINCIPAL DISPLAY PANEL - 20 mL Vial Carton

NDC 0955-1733-20 Rx only

OXALIplatin injection

100 mg / 20 mL
(5 mg/mL)

For Intravenous Infusion After Dilution

Warning: Cytotoxic Agent
See full prescribing information.

DO NOT MIX OR ADD TO
SODIUM CHLORIDE/
CHLORIDE-CONTAINING
SOLUTIONS

One single-dose vial

PREMIERProRx®